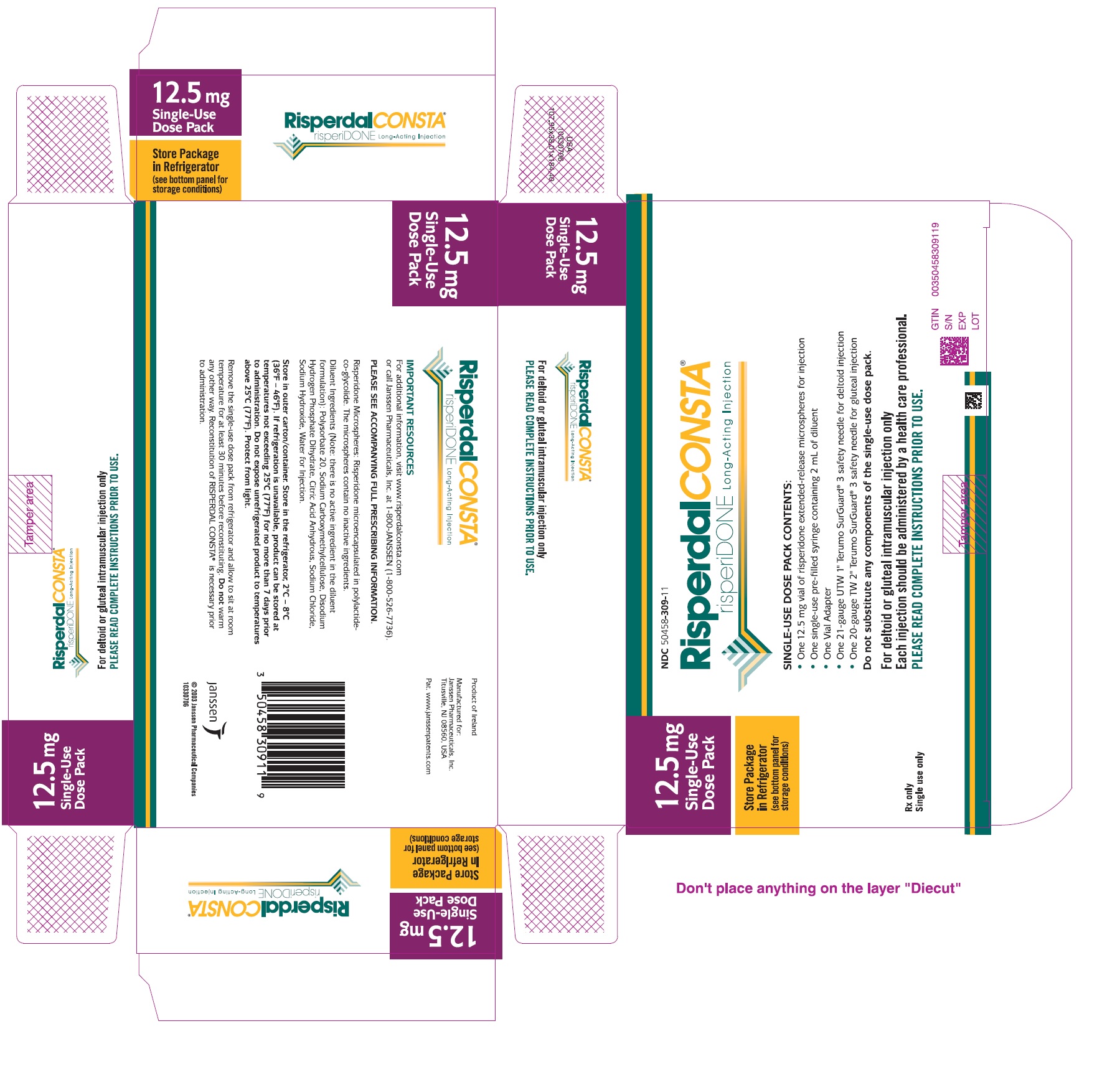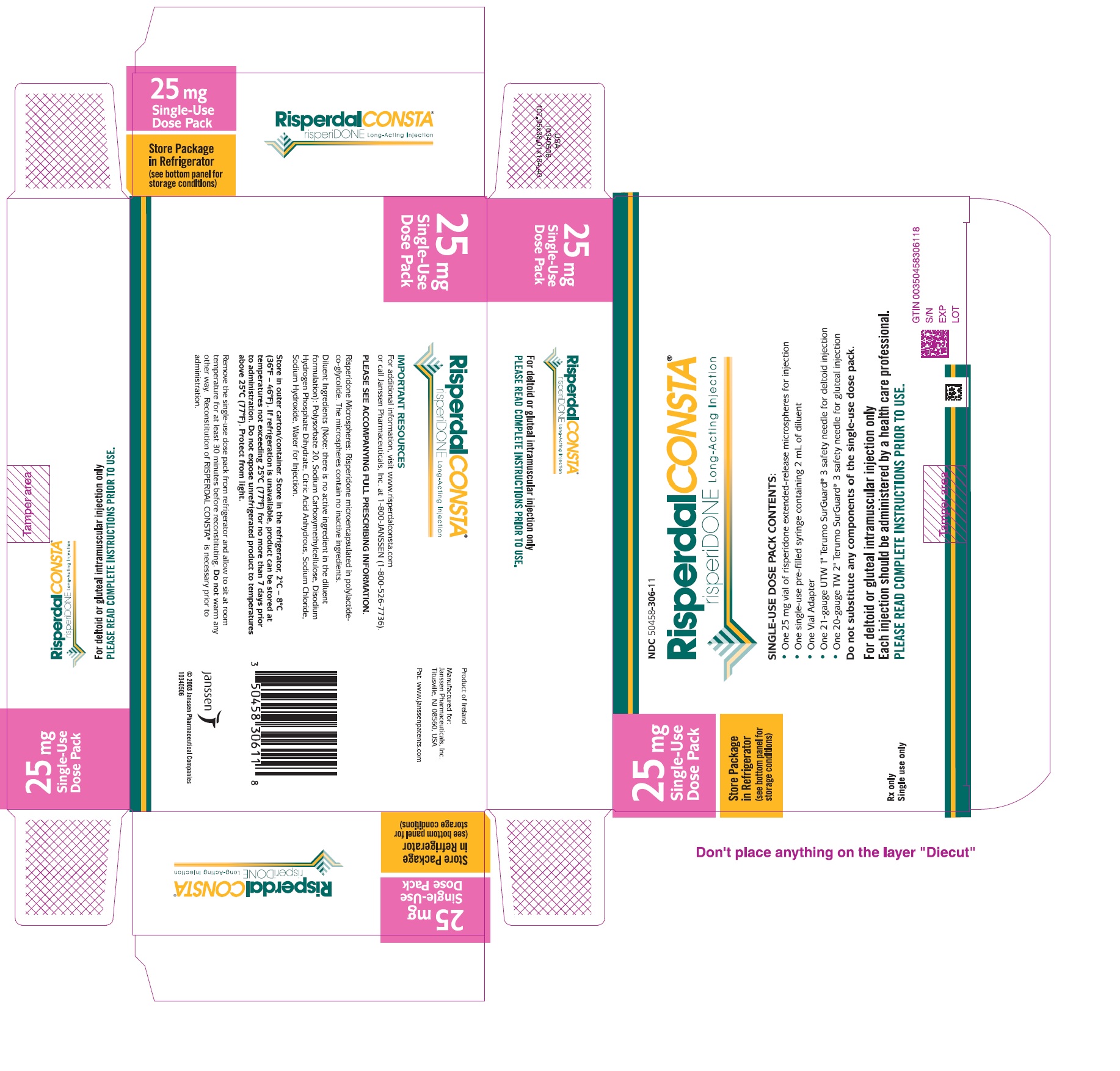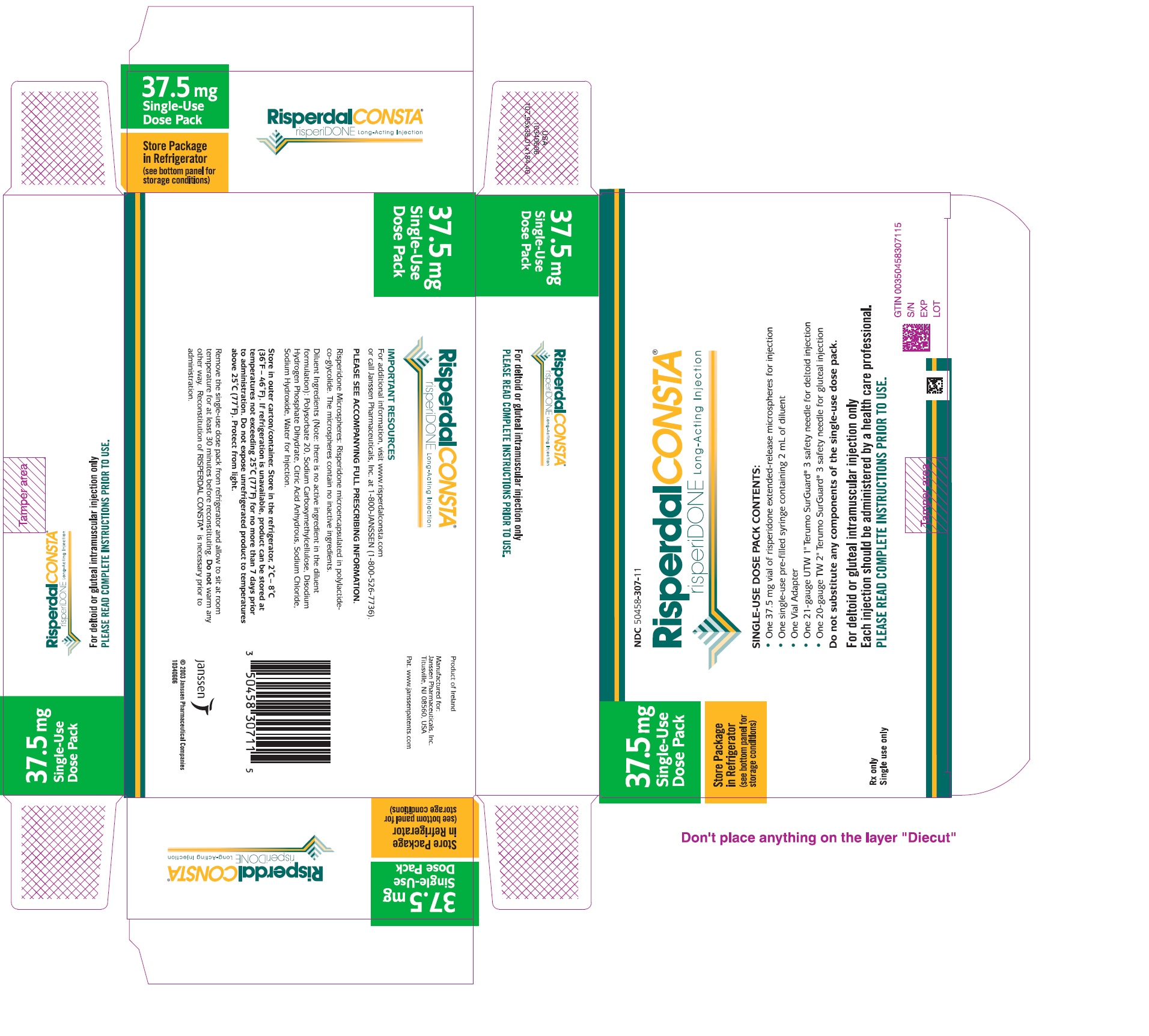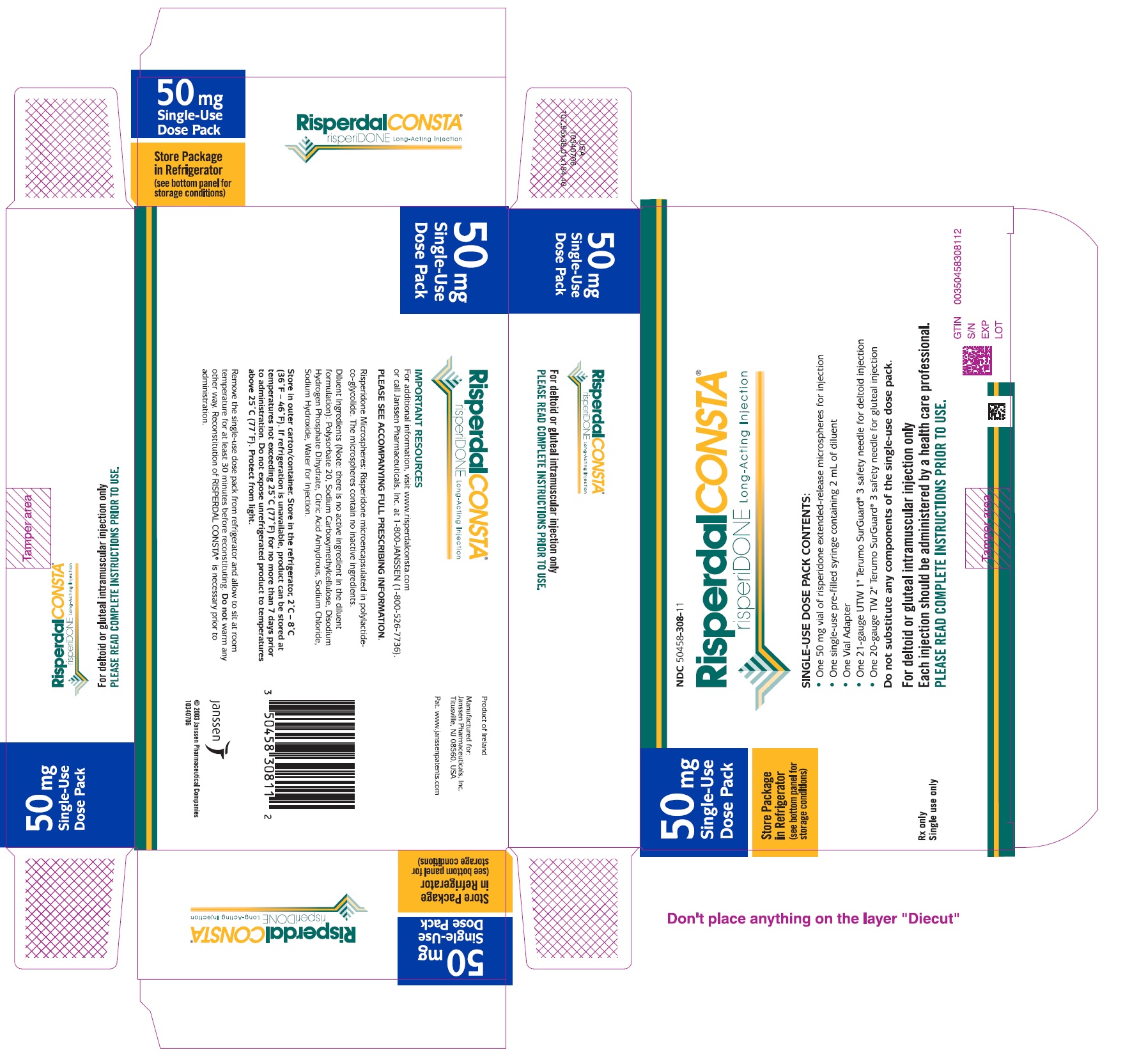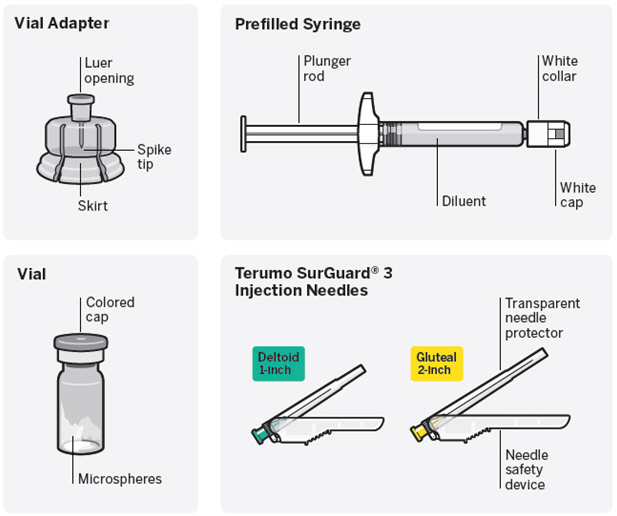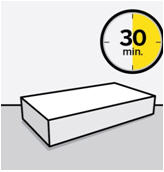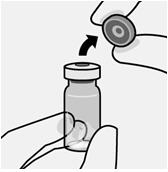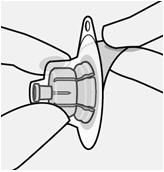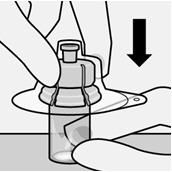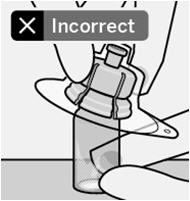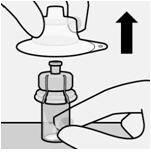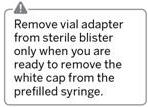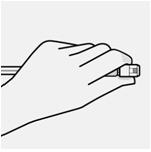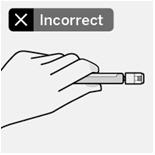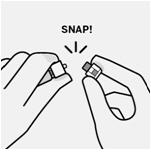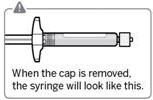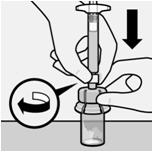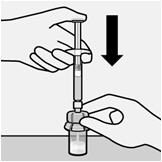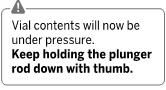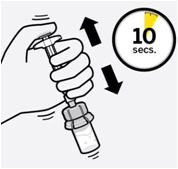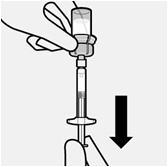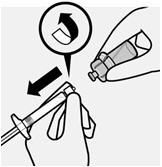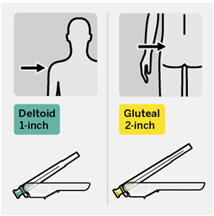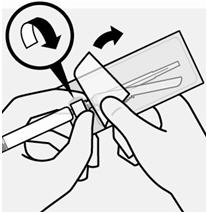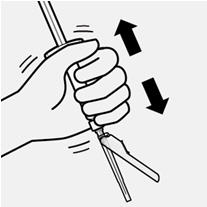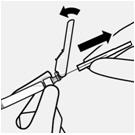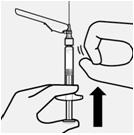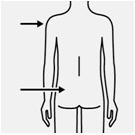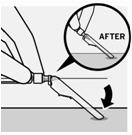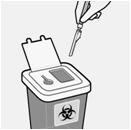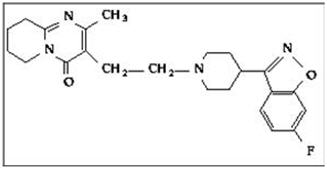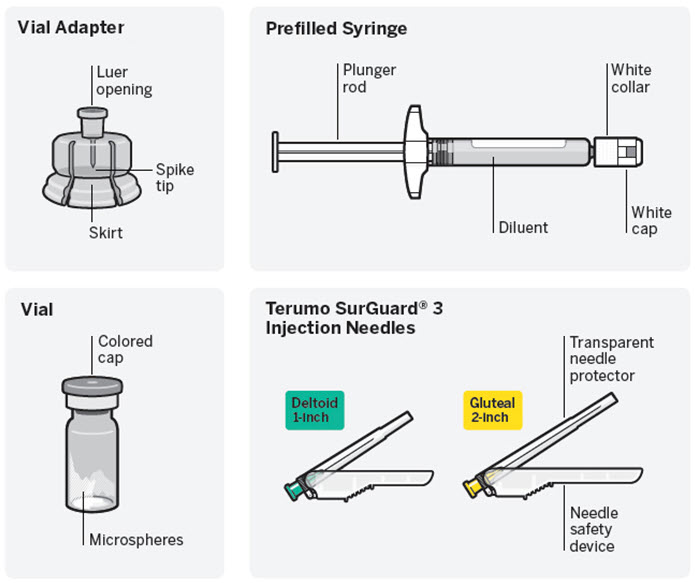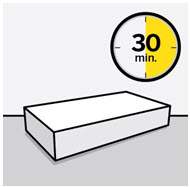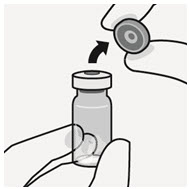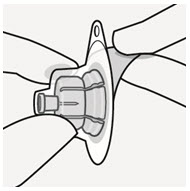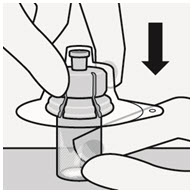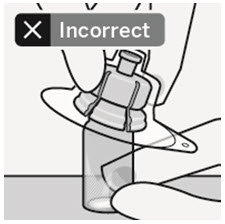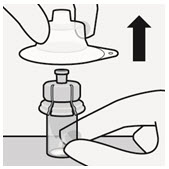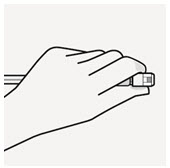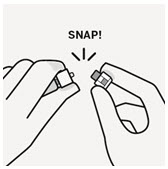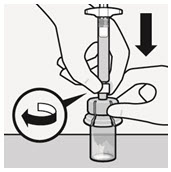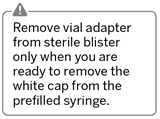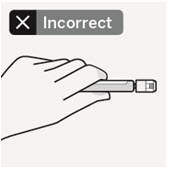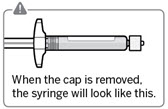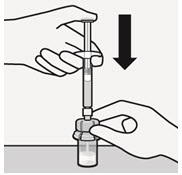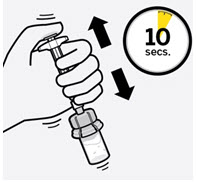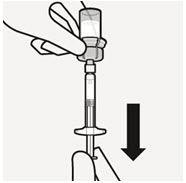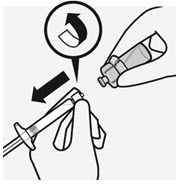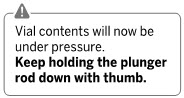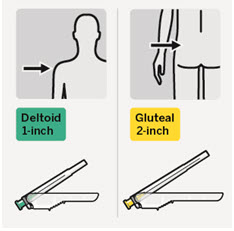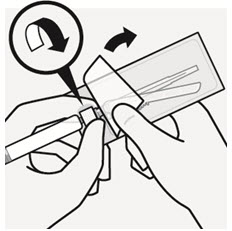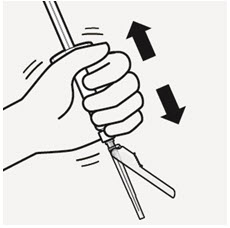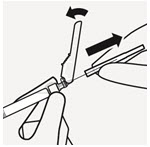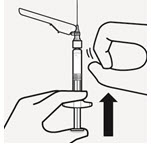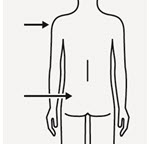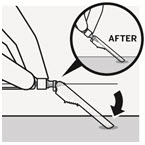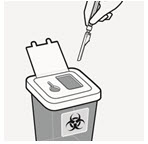 DRUG LABEL: RISPERDAL CONSTA
NDC: 50458-309 | Form: KIT | Route: INTRAMUSCULAR
Manufacturer: Janssen Pharmaceuticals, Inc.
Category: prescription | Type: HUMAN PRESCRIPTION DRUG LABEL
Date: 20251105

ACTIVE INGREDIENTS: RISPERIDONE 12.5 mg/2 mL
INACTIVE INGREDIENTS: POLYSORBATE 20; CARBOXYMETHYLCELLULOSE SODIUM, UNSPECIFIED; SODIUM PHOSPHATE, DIBASIC, HEPTAHYDRATE; ANHYDROUS CITRIC ACID; SODIUM CHLORIDE; SODIUM HYDROXIDE; WATER

HIGHLIGHTS OF PRESCRIBING INFORMATION

These highlights do not include all the information needed to use RISPERDAL CONSTA® safely and effectively. See full prescribing information for RISPERDAL CONSTA®..
RISPERDAL CONSTA® (risperidone) LONG-ACTING INJECTION
Initial U.S. Approval: 2003

WARNING: INCREASED MORTALITY IN ELDERLY PATIENTS WITH DEMENTIA-RELATED PSYCHOSIS

See full prescribing information for complete boxed warning.

Elderly patients with dementia-related psychosis treated with antipsychotic drugs are at an increased risk of death. RISPERDAL CONSTA is not approved for use in patients with dementia-related psychosis. (5.1)

RECENT MAJOR CHANGES

Warnings and Precautions (5.6) | 1/2025

1 INDICATIONS AND USAGE

RISPERDAL CONSTA is an atypical antipsychotic indicated:

- for the treatment of schizophrenia. (1.1)
- as monotherapy or as adjunctive therapy to lithium or valproate for the maintenance treatment of Bipolar I Disorder. (1.2)

2 DOSAGE AND ADMINISTRATION

- For patients who have never taken oral RISPERDAL, tolerability should be established with oral RISPERDAL prior to initiating treatment with RISPERDAL CONSTA. (2)
- Administer by deep intramuscular (IM) deltoid or gluteal injection. Each injection should be administered by a health care professional using the appropriate enclosed safety needle (1-inch for deltoid administration alternating injections between the two arms and 2-inch for gluteal administration alternating injections between the two buttocks). Do not administer intravenously. (2)
- 25 mg intramuscular (IM) every 2 weeks. Patients not responding to 25 mg may benefit from a higher dose of 37.5 mg or 50 mg. The maximum dose should not exceed 50 mg every 2 weeks. (2)
- Oral RISPERDAL (or another antipsychotic medication) should be given with the first injection of RISPERDAL CONSTA, and continued for 3 weeks (and then discontinued) to ensure adequate therapeutic plasma concentrations from RISPERDAL CONSTA. (2)
- Upward dose adjustment of RISPERDAL CONSTA should not be made more frequently than every 4 weeks. Clinical effects of each upward dose adjustment should not be anticipated earlier than 3 weeks after injection. (2)
- Avoid inadvertent administration into a blood vessel. (5.16)
- See Full Prescribing Information Section 2.8for instructions for use.

3 DOSAGE FORMS AND STRENGTHS

Vial kits: 12.5 mg, 25 mg, 37.5 mg, and 50 mg (3)

4 CONTRAINDICATIONS

- Known hypersensitivity to risperidone, paliperidone, or to any excipients in RISPERDAL CONSTA. (4)

5 WARNINGS AND PRECAUTIONS

- Cerebrovascular events, including stroke, in elderly patients with dementia-related psychosis. RISPERDAL CONSTA is not approved for use in patients with dementia-related psychosis (5.2)
- Neuroleptic Malignant Syndrome: Manage with immediate discontinuation and close monitoring (5.3)
- Tardive Dyskinesia: Discontinue treatment if clinically appropriate (5.4)
- Metabolic Changes: Atypical antipsychotic drugs have been associated with metabolic changes that may increase cardiovascular/ cerebrovascular risk. These metabolic changes include hyperglycemia, dyslipidemia, and weight gain. (5.5)
  - Hyperglycemia and Diabetes Mellitus:Monitor patients for symptoms of hyperglycemia including polydipsia, polyuria, polyphagia, and weakness. Monitor glucose regularly in patients with diabetes or at risk for diabetes. (5.5)
  - Dyslipidemia:Undesirable alterations have been observed in patients treated with atypical antipsychotics. (5.5)
  - Weight Gain:Significant weight gain has been reported. Monitor weight gain. (5.5)
- Hyperprolactinemia: Risperidone treatment may elevate prolactin levels. Long-standing hyperprolactinemia, when associated with hypogonadism, can lead to decreased bone density in men and women. (5.6)
- Orthostatic hypotension: associated with dizziness, tachycardia, bradycardia, and syncope can occur, especially during initial dose titration with oral risperidone. Use caution in patients with cardiovascular disease, cerebrovascular disease, and conditions that could affect hemodynamic responses. (5.7)
- Leukopenia, Neutropenia, and Agranulocytosis have been reported with antipsychotics, including RISPERDAL CONSTA. Patients with history of a clinically significant low white blood cell count (WBC) or a drug-induced leukopenia/neutropenia should have their complete blood cell count (CBC) monitored frequently during the first few months of therapy and discontinuation of RISPERDAL CONSTA should be considered at the first sign of a clinically significant decline in WBC in the absence of other causative factors. (5.9)
- Potential for cognitive and motor impairment: has potential to impair judgment, thinking, and motor skills. Use caution when operating machinery, including automobiles. (5.10)
- Seizures: Use cautiously in patients with a history of seizures or with conditions that potentially lower the seizure threshold. (5.11)
- Dysphagia: Esophageal dysmotility and aspiration can occur. Use cautiously in patients at risk for aspiration pneumonia. (5.12)
- Priapism: has been reported. Severe priapism may require surgical intervention. (5.13)
- Avoid inadvertent administration into a blood vessel. (5.15)

6 ADVERSE REACTIONS

The most common adverse reactions in clinical trials in patients with schizophrenia (≥ 5%) were headache, parkinsonism, dizziness, akathisia, fatigue, constipation, dyspepsia, sedation, weight increased, pain in extremity, and dry mouth. The most common adverse reactions in clinical trials in patients with bipolar disorder were weight increased (5% in monotherapy trial) and tremor and parkinsonism (≥ 10% in adjunctive therapy trial). (6)

The most common adverse reactions that were associated with discontinuation from clinical trials in patients with schizophrenia were agitation, depression, anxiety, and akathisia. Adverse reactions that were associated with discontinuation from bipolar disorder trials were hyperglycemia (one subject monotherapy trial) and hypokinesia and tardive dyskinesia (one subject each in adjunctive therapy trial). (6)

To report SUSPECTED ADVERSE REACTIONS, contact Janssen Pharmaceuticals, Inc. 1-800-526-7736 or FDA at 1-800-FDA-1088 or www.fda.gov/medwatch.

7 DRUG INTERACTIONS

- Due to CNS effects, use caution when administering with other centrally-acting drugs. Avoid alcohol. (7.1)
- Due to hypotensive effects, hypotensive effects of other drugs with this potential may be enhanced. (7.2)
- Effects of levodopa and dopamine agonists may be antagonized. (7.3)
- Cimetidine and ranitidine increase the bioavailability of risperidone. (7.5)
- Clozapine may decrease clearance of risperidone. (7.7)
- Fluoxetine and paroxetine increase plasma concentrations of risperidone. (7.12)
- Carbamazepine and other enzyme inducers decrease plasma concentrations of risperidone. (7.13)

8 USE IN SPECIFIC POPULATIONS

- Pregnancy: May cause extrapyramidal and/or withdrawal symptoms in neonates with third trimester exposure. (8.1)
- Renal or Hepatic Impairment: dose appropriately with oral RISPERDAL prior to initiating treatment with RISPERDAL CONSTA. A lower starting dose of RISPERDAL CONSTA of 12.5 mg may be appropriate in some patients. (2.4)
- Pediatric Use: safety and effectiveness not established in patients less than 18 years of age. (8.4)
- Elderly: dosing for otherwise healthy elderly patients is the same as for healthy nonelderly. Elderly may be more predisposed to orthostatic effects than nonelderly. (8.5)

FULL PRESCRIBING INFORMATION

WARNING: INCREASED MORTALITY IN ELDERLY PATIENTS WITH DEMENTIA-RELATED PSYCHOSIS

Elderly patients with dementia-related psychosis treated with antipsychotic drugs are at an increased risk of death. RISPERDAL CONSTA is not approved for the treatment of patients with dementia-related psychosis. [see Warnings and Precautions (5.1)]

1 INDICATIONS AND USAGE

1.1 Schizophrenia

RISPERDAL CONSTA (risperidone) is indicated for the treatment of schizophrenia [see Clinical Studies (14.1)].

1.2 Bipolar Disorder

RISPERDAL CONSTA is indicated as monotherapy or as adjunctive therapy to lithium or valproate for the maintenance treatment of Bipolar I Disorder [see Clinical Studies (14.2, 14.3)] .

2 DOSAGE AND ADMINISTRATION

For patients who have never taken oral RISPERDAL, it is recommended to establish tolerability with oral RISPERDAL prior to initiating treatment with RISPERDAL CONSTA.

RISPERDAL CONSTA should be administered every 2 weeks by deep intramuscular (IM) deltoid or gluteal injection. Each injection should be administered by a health care professional using the appropriate enclosed safety needle [see Dosage and Administration (2.8)] . For deltoid administration, use the 1-inch needle alternating injections between the two arms. For gluteal administration, use the 2-inch needle alternating injections between the two buttocks. Do not administer intravenously.

2.1 Schizophrenia

The recommended dose for the treatment of schizophrenia is 25 mg IM every 2 weeks. Although dose response for effectiveness has not been established for RISPERDAL CONSTA, some patients not responding to 25 mg may benefit from a higher dose of 37.5 mg or 50 mg. The maximum dose should not exceed 50 mg RISPERDAL CONSTA every 2 weeks. No additional benefit was observed with dosages greater than 50 mg RISPERDAL CONSTA; however, a higher incidence of adverse effects was observed.

The efficacy of RISPERDAL CONSTA in the treatment of schizophrenia has not been evaluated in controlled clinical trials for longer than 12 weeks. Although controlled studies have not been conducted to answer the question of how long patients with schizophrenia should be treated with RISPERDAL CONSTA, oral risperidone has been shown to be effective in delaying time to relapse in longer-term use. It is recommended that responding patients be continued on treatment with RISPERDAL CONSTA at the lowest dose needed. The physician who elects to use RISPERDAL CONSTA for extended periods should periodically re-evaluate the long-term risks and benefits of the drug for the individual patient.

2.2 Bipolar Disorder

The recommended dose for monotherapy or adjunctive therapy to lithium or valproate for the maintenance treatment of Bipolar I Disorder is 25 mg IM every 2 weeks. Some patients may benefit from a higher dose of 37.5 mg or 50 mg. Dosages above 50 mg have not been studied in this population. The physician who elects to use RISPERDAL CONSTA for extended periods should periodically re-evaluate the long-term risks and benefits of the drug for the individual patient.

2.3 General Dosing Information

A lower initial dose of 12.5 mg may be appropriate when clinical factors warrant dose adjustment, such as in patients with hepatic or renal impairment, for certain drug interactions that increase risperidone plasma concentrations [see Drug Interactions (7.11)] or in patients who have a history of poor tolerability to psychotropic medications. The efficacy of the 12.5 mg dose has not been investigated in clinical trials.

Oral RISPERDAL (or another antipsychotic medication) should be given with the first injection of RISPERDAL CONSTA and continued for 3 weeks (and then discontinued) to ensure that adequate therapeutic plasma concentrations are maintained prior to the main release phase of risperidone from the injection site [see Clinical Pharmacology (12.3)] .

Upward dose adjustment should not be made more frequently than every 4 weeks. The clinical effects of this dose adjustment should not be anticipated earlier than 3 weeks after the first injection with the higher dose.

In patients with clinical factors such as hepatic or renal impairment or certain drug interactions that increase risperidone plasma concentrations [see Drug Interactions (7.11)] , dose reduction as low as 12.5 mg may be appropriate. The efficacy of the 12.5 mg dose has not been investigated in clinical trials.

Do not combine two different dose strengths of RISPERDAL CONSTA in a single administration.

2.4 Dosage in Special Populations

Elderly

For elderly patients treated with RISPERDAL CONSTA, the recommended dosage is 25 mg IM every 2 weeks. Oral RISPERDAL (or another antipsychotic medication) should be given with the first injection of RISPERDAL CONSTA and should be continued for 3 weeks to ensure that adequate therapeutic plasma concentrations are maintained prior to the main release phase of risperidone from the injection site [see Clinical Pharmacology (12.3)] .

Renal or Hepatic Impairment

Patients with renal or hepatic impairment should be treated with titrated doses of oral RISPERDAL prior to initiating treatment with RISPERDAL CONSTA. The recommended starting dose is 0.5 mg oral RISPERDAL twice daily during the first week, which can be increased to 1 mg twice daily or 2 mg once daily during the second week. If a total daily dose of at least 2 mg oral RISPERDAL is well tolerated, an injection of 25 mg RISPERDAL CONSTA can be administered every 2 weeks. Oral supplementation should be continued for 3 weeks after the first injection until the main release of risperidone from the injection site has begun. In some patients, slower titration may be medically appropriate. Alternatively, a starting dose of RISPERDAL CONSTA of 12.5 mg may be appropriate. The efficacy of the 12.5 mg dose has not been investigated in clinical trials.

Patients with renal impairment may have less ability to eliminate risperidone than normal adults. Patients with impaired hepatic function may have an increase in the free fraction of the risperidone, possibly resulting in an enhanced effect [see Clinical Pharmacology (12.3)] . Elderly patients and patients with a predisposition to hypotensive reactions or for whom such reactions would pose a particular risk should be instructed in nonpharmacologic interventions that help to reduce the occurrence of orthostatic hypotension (e.g., sitting on the edge of the bed for several minutes before attempting to stand in the morning and slowly rising from a seated position). These patients should avoid sodium depletion or dehydration, and circumstances that accentuate hypotension (alcohol intake, high ambient temperature, etc.). Monitoring of orthostatic vital signs should be considered [see Warnings and Precautions (5.7)] .

2.5 Reinitiation of Treatment in Patients Previously Discontinued

There are no data to specifically address reinitiation of treatment. When restarting patients who have had an interval off treatment with RISPERDAL CONSTA, supplementation with oral RISPERDAL (or another antipsychotic medication) should be administered.

2.6 Switching from Other Antipsychotics

There are no systematically collected data to specifically address switching patients from other antipsychotics to RISPERDAL CONSTA, or concerning concomitant administration with other antipsychotics. Previous antipsychotics should be continued for 3 weeks after the first injection of RISPERDAL CONSTA to ensure that therapeutic concentrations are maintained until the main release phase of risperidone from the injection site has begun [see Clinical Pharmacology (12.3)] . For patients who have never taken oral RISPERDAL, it is recommended to establish tolerability with oral RISPERDAL prior to initiating treatment with RISPERDAL CONSTA. As recommended with other antipsychotic medications, the need for continuing existing EPS medication should be re-evaluated periodically.

2.7 Co-Administration of RISPERDAL CONSTA with Certain Other Medications

Co-administration of carbamazepine and other CYP 3A4 enzyme inducers (e.g., phenytoin, rifampin, phenobarbital) with risperidone would be expected to cause decreases in the plasma concentrations of the sum of risperidone and 9-hydroxyrisperidone combined, which could lead to decreased efficacy of RISPERDAL CONSTA treatment. The dose of risperidone needs to be titrated accordingly for patients receiving these enzyme inducers, especially during initiation or discontinuation of therapy with these inducers [see Drug Interactions (7.11)] . At the initiation of therapy with carbamazepine or other known CYP 3A4 hepatic enzyme inducers, patients should be closely monitored during the first 4–8 weeks, since the dose of RISPERDAL CONSTA may need to be adjusted. A dose increase, or additional oral RISPERDAL, may need to be considered. On discontinuation of carbamazepine or other CYP 3A4 hepatic enzyme inducers, the dosage of RISPERDAL CONSTA should be re-evaluated and, if necessary, decreased. Patients may be placed on a lower dose of RISPERDAL CONSTA between 2 to 4 weeks before the planned discontinuation of carbamazepine or other CYP 3A4 inducers to adjust for the expected increase in plasma concentrations of risperidone plus 9-hydroxyrisperidone. For patients treated with the recommended dose of 25 mg RISPERDAL CONSTA and discontinuing from carbamazepine or other CYP3A4 enzyme inducers, it is recommended to continue treatment with the 25-mg dose unless clinical judgment necessitates lowering the RISPERDAL CONSTA dose to 12.5 mg or necessitates interruption of RISPERDAL CONSTA treatment. The efficacy of the 12.5 mg dose has not been investigated in clinical trials.

Fluoxetine and paroxetine, CYP 2D6 inhibitors, have been shown to increase the plasma concentration of risperidone 2.5–2.8 fold and 3–9 fold respectively. Fluoxetine did not affect the plasma concentration of 9-hydroxyrisperidone. Paroxetine lowered the concentration of 9-hydroxyrisperidone by about 10%. The dose of risperidone needs to be titrated accordingly when fluoxetine or paroxetine is co-administered. When either concomitant fluoxetine or paroxetine is initiated or discontinued, the physician should re-evaluate the dose of RISPERDAL CONSTA. When initiation of fluoxetine or paroxetine is considered, patients may be placed on a lower dose of RISPERDAL CONSTA between 2 to 4 weeks before the planned start of fluoxetine or paroxetine therapy to adjust for the expected increase in plasma concentrations of risperidone. When fluoxetine or paroxetine is initiated in patients receiving the recommended dose of 25 mg RISPERDAL CONSTA, it is recommended to continue treatment with the 25 mg dose unless clinical judgment necessitates lowering the RISPERDAL CONSTA dose to 12.5 mg or necessitates interruption of RISPERDAL CONSTA treatment. When RISPERDAL CONSTA is initiated in patients already receiving fluoxetine or paroxetine, a starting dose of 12.5 mg can be considered. The efficacy of the 12.5 mg dose has not been investigated in clinical trials. The effects of discontinuation of concomitant fluoxetine or paroxetine therapy on the pharmacokinetics of risperidone and 9-hydroxyrisperidone have not been studied. [see Drug Interactions (7.11)] .

2.8 Instructions for Use

For deltoid or gluteal intramuscular injection only

IMPORTANT RESOURCES

For additional information, visit www.risperdalconsta.com or call Janssen Pharmaceuticals, Inc. at 1-800-526-7736.

Important Information

RISPERDAL CONSTA requires close attention to these step-by-step Instructions for Use to help ensure successful administration.

Use components provided

The components in this dose pack are specifically designed for use with RISPERDAL CONSTA. RISPERDAL CONSTA must be reconstituted only in the diluent supplied in the dose pack.

Do notsubstitute ANY components of the dose pack.

Do not store suspension after reconstitution

Administer dose as soon as possible after reconstitution to avoid settling.

Proper dosing

The entire contents of the vial must be administered to ensure intended dose of RISPERDAL CONSTA is delivered.

SINGLE-USE DEVICE

Do not reuse.Medical devices require specific material characteristics to perform as intended. These characteristics have been verified for single use only. Any attempt to re-process the device for subsequent re-use may adversely affect the integrity of the device or lead to deterioration in performance.

Dose pack contents

Step 1 Assemble components
Take out dose pack Connect vial adapter to vial
Wait 30 minutes Remove dose pack from the refrigerator and allow to sit at room temperature for at least 30 minutesbefore reconstituting. Do notwarm any other way. | Remove cap from vial Flip off colored cap from vial. Wipe top of the grey stopper with an alcohol swab. Allow to air dry. Do notremove grey rubber stopper. | Prepare vial adapter Hold sterile blister as shown. Peel back and remove paper backing. Do notremove vial adapter from blister. Do nottouch spike tip at any time. This will result in contamination. | Connect vial adapter to vial Place vial on a hard surface and hold by the base. Center vial adapter over the grey rubber stopper. Push vial adapter straight down onto vial top until it snaps securely into place. Do notplace vial adapter on at an angle or diluent may leak upon transfer to the vial.
Connect prefilled syringe to vial adapter
Remove sterile blister; Keep vial vertical to prevent leakage. Hold base of vial and pull up on the sterile blister to remove. Do notshake. Do nottouch exposed luer opening on vial adapter. This will result in contamination. | Use proper grip Hold by white collar at the tip of the syringe. Do nothold syringe by the glass barrel during assembly. | Remove cap Holding the white collar, snap off the white cap. Do nottwist or cut off the white cap. Do nottouch syringe tip. This will result in contamination.; The broken-off cap can be discarded. | Connect syringe to vial adapter Hold vial adapter by skirt to keep stationary. Hold syringe by white collarthen insert tip into the luer opening of the vial adapter. Do nothold the glass syringe barrel. This may cause the white collar to loosen or detach. Attach the syringe to the vial adapter with a firm clockwise twisting motionuntil it feels snug. Do notover-tighten. Over-tightening may cause the syringe tip to break.

Step 2 Reconstitute microspheres

Inject diluent
Inject entire amount of diluent from syringe into the vial.

Suspend microspheres in diluent
Continuing to hold down the plunger rod, shake vigorously for at least 10 seconds, as shown.
Check the suspension. When properly mixed, the suspension appears uniform, thick and milky in color. Microspheres will be visible in the liquid.
Immediately proceed to the next step so suspension does not settle.

Transfer suspension to syringe
Invert vial completely. Slowly pull plunger rod down to withdraw entire contents from the vial into the syringe.

Remove vial adapter
Hold white collar on the syringe and unscrew from vial adapter.
Tear section of the vial label at the perforation. Apply detached label to the syringe for identification purposes.
Discard both vial and vial adapter appropriately.

Step 3 Attach needle

Select appropriate needle
Choose needle based on injection location (gluteal or deltoid).

Attach needle
Peel blister pouch open part way and use to grasp the base of the needle, as shown.
Holding the white collar on the syringe, attach syringe to needle luer connection with a firm clockwise twisting motionuntil snug.
Do nottouch needle luer opening. This will result in contamination.

Resuspend microspheres
Fully remove the blister pouch.
Just before injection, shake syringe vigorously again, as some settling will have occurred.

Step 4 Inject dose

Remove transparent needle protector
Move the needle safety device back towards the syringe, as shown. Then hold white collar on syringe and carefully pull the transparent needle protector straight off.
Do nottwist transparent needle protector, as the luer connection may loosen.

Remove air bubbles
Hold needle upright and tap gently to make any air bubbles rise to the top.
Slowly and carefully press plunger rod upward to remove air.

Inject
Immediately inject entire contents of syringe intramuscularly (IM) into the gluteal or deltoid muscle of the patient.
Gluteal injection should be made into the upper-outer quadrant of the gluteal area.
Do not administer intravenously.

Secure needle in safety device
Using one hand, place needle safety device at a 45-degree angle on a hard, flat surface. Press down with a firm, quick motion until needle is fully engaged in safety device.
Avoid needle stick injury:
Do notuse two hands.
Do notintentionally disengage or mishandle the needle safety device.
Do notattempt to straighten the needle or engage the safety device if the needle is bent or damaged.

Properly dispose of needles
Check to confirm needle safety device is fully engaged.
Discard in an approved sharps container.
Also discard the unused needle provided in the dose pack.

3 DOSAGE FORMS AND STRENGTHS

RISPERDAL CONSTA is available in dosage strengths of 12.5 mg, 25 mg, 37.5 mg, and 50 mg risperidone. It is provided as a single-use dose pack, consisting of a vial containing the risperidone microspheres, a pre-filled syringe containing 2 mL of diluent for RISPERDAL CONSTA, a vial adapter, and two Terumo SurGuard 3 Needles for intramuscular injection (a 21 G UTW 1-inch needle with needle protection device for deltoid administration and a 20 G TW 2-inch needle with needle protection device for gluteal administration).

4 CONTRAINDICATIONS

RISPERDAL CONSTA is contraindicated in patients with a known hypersensitivity to either risperidone or paliperidone, or to any of the excipients in the RISPERDAL CONSTA formulation. Hypersensitivity reactions, including anaphylactic reactions and angioedema, have been reported in patients treated with risperidone and in patients treated with paliperidone. Paliperidone is a metabolite of risperidone.

5 WARNINGS AND PRECAUTIONS

5.1 Increased Mortality in Elderly Patients with Dementia-Related Psychosis

Elderly patients with dementia-related psychosis treated with antipsychotic drugs are at an increased risk of death. Analyses of 17 placebo-controlled trials (modal duration of 10 weeks), largely in patients taking atypical antipsychotic drugs, revealed a risk of death in drug-treated patients of between 1.6 to 1.7 times the risk of death in placebo-treated patients. Over the course of a typical 10-week controlled trial, the rate of death in drug-treated patients was about 4.5%, compared to a rate of about 2.6% in the placebo group. Although the causes of death were varied, most of the deaths appeared to be either cardiovascular (e.g., heart failure, sudden death) or infectious (e.g., pneumonia) in nature. Observational studies suggest that, similar to atypical antipsychotic drugs, treatment with conventional antipsychotic drugs may increase mortality. The extent to which the findings of increased mortality in observational studies may be attributed to the antipsychotic drug as opposed to some characteristic(s) of the patients is not clear.

RISPERDAL CONSTA (risperidone) is not approved for the treatment of dementia-related psychosis [see Boxed Warning] .

5.2 Cerebrovascular Adverse Events, Including Stroke, in Elderly Patients with Dementia-Related Psychosis

Cerebrovascular adverse events (e.g., stroke, transient ischemic attack), including fatalities, were reported in patients (mean age 85 years; range 73–97) in trials of oral risperidone in elderly patients with dementia-related psychosis. In placebo-controlled trials, there was a significantly higher incidence of cerebrovascular adverse events in patients treated with oral risperidone compared to patients treated with placebo. RISPERDAL CONSTA is not approved for the treatment of patients with dementia-related psychosis. [See also Boxed Warningand Warnings and Precautions (5.1)]

5.3 Neuroleptic Malignant Syndrome

Neuroleptic Malignant Syndrome (NMS), a potentially fatal symptom complex, has been reported in association with antipsychotic drugs. Clinical manifestations of NMS are hyperpyrexia, muscle rigidity, altered mental status including delirium, and autonomic instability (irregular pulse or blood pressure, tachycardia, diaphoresis, and cardiac dysrhythmia). Additional signs may include elevated creatine phosphokinase, myoglobinuria (rhabdomyolysis), and acute renal failure.

If NMS is suspected, immediately discontinue RISPERDAL CONSTA and provide symptomatic treatment and monitoring.

5.4 Tardive Dyskinesia

Tardive dyskinesia, a syndrome consisting of potentially irreversible, involuntary, dyskinetic movements, may develop in patients treated with antipsychotic drugs. Although the prevalence of the syndrome appears to be highest among the elderly, especially elderly women, it is impossible to predict which patients will develop the syndrome. Whether antipsychotic drug products differ in their potential to cause tardive dyskinesia is unknown.

The risk of developing tardive dyskinesia and the likelihood that it will become irreversible increase with the duration of treatment and the cumulative dose. The syndrome can develop after relatively brief treatment periods, even at low doses. It may also occur after discontinuation of treatment.

Tardive dyskinesia may remit, partially or completely, if antipsychotic treatment is discontinued. Antipsychotic treatment, itself, however, may suppress (or partially suppress) the signs and symptoms of the syndrome, possibly masking the underlying process. The effect that symptomatic suppression has upon the long-term course of the syndrome is unknown.

Given these considerations, RISPERDAL CONSTA should be prescribed in a manner that is most likely to minimize the occurrence of tardive dyskinesia. Chronic antipsychotic treatment should generally be reserved for patients: (1) who suffer from a chronic illness that is known to respond to antipsychotic drugs, and (2) for whom alternative, equally effective, but potentially less harmful treatments are not available or appropriate. In patients who do require chronic treatment, the lowest dose and the shortest duration of treatment producing a satisfactory clinical response. Periodically reassess the need for continued treatment.

If signs and symptoms of tardive dyskinesia appear in a patient treated with RISPERDAL CONSTA, drug discontinuation should be considered. However, some patients may require treatment with RISPERDAL CONSTA despite the presence of the syndrome.

5.5 Metabolic Changes

Atypical antipsychotic drugs have been associated with metabolic changes that may increase cardiovascular/cerebrovascular risk. These metabolic changes include hyperglycemia, dyslipidemia, and body weight gain. While all of the drugs in the class have been shown to produce some metabolic changes, each drug has its own specific risk profile.

Hyperglycemia and Diabetes Mellitus

Hyperglycemia and diabetes mellitus, in some cases extreme and associated with ketoacidosis or hyperosmolar coma or death, have been reported in patients treated with atypical antipsychotics including RISPERDAL. Assessment of the relationship between atypical antipsychotic use and glucose abnormalities is complicated by the possibility of an increased background risk of diabetes mellitus in patients with schizophrenia and the increasing incidence of diabetes mellitus in the general population. Given these confounders, the relationship between atypical antipsychotic use and hyperglycemia-related adverse events is not completely understood. However, epidemiological studies suggest an increased risk of treatment-emergent hyperglycemia-related adverse events in patients treated with the atypical antipsychotics. Precise risk estimates for hyperglycemia-related adverse events in patients treated with atypical antipsychotics are not available.

Patients with an established diagnosis of diabetes mellitus who are started on atypical antipsychotics, including RISPERDAL, should be monitored regularly for worsening of glucose control. Patients with risk factors for diabetes mellitus (e.g., obesity, family history of diabetes) who are starting treatment with atypical antipsychotics, including RISPERDAL, should undergo fasting blood glucose testing at the beginning of treatment and periodically during treatment. Any patient treated with atypical antipsychotics, including RISPERDAL, should be monitored for symptoms of hyperglycemia including polydipsia, polyuria, polyphagia, and weakness. Patients who develop symptoms of hyperglycemia during treatment with atypical antipsychotics, including RISPERDAL, should undergo fasting blood glucose testing. In some cases, hyperglycemia has resolved when the atypical antipsychotic, including RISPERDAL, was discontinued; however, some patients required continuation of anti-diabetic treatment despite discontinuation of RISPERDAL.

Pooled data from 3 double-blind, placebo-controlled studies in subjects with schizophrenia and 4 double-blind, placebo-controlled monotherapy studies in subjects with bipolar mania with oral risperidone are presented in Table 1.

Table 1. Change in Random Glucose From Seven Placebo-Controlled, 3- to 8-Week, Fixed- or Flexible-Dose Studies in Adult Subjects With Schizophrenia or Bipolar Mania With Oral Risperidone
 |  | RISPERDAL
 | Placebo | 1–8 mg/day | >8–16 mg/day
 | Mean change from baseline (mg/dL)
 | N=555 | N=748 | N=164
Serum Glucose | -1.4 | 0.8 | 0.6
 | Proportion of patients with shifts
Serum Glucose | 0.6% | 0.4% | 0%
(<140 mg/dL to ≥200 mg/dL) | (3/525) | (3/702) | (0/158)

In longer-term, controlled and uncontrolled studies in adult subjects, RISPERDAL was associated with a mean change in glucose of +2.8 mg/dL at Week 24 (N=151) and +4.1 mg/dL at Week 48 (N=50).

Dyslipidemia

Undesirable alterations in lipids have been observed in patients treated with atypical antipsychotics.

Pooled data from 7 placebo-controlled, 3- to 8- week, fixed- or flexible-dose studies in adult subjects with schizophrenia or bipolar mania are presented in Table 2.

Table 2. Change in Random Lipids From Seven Placebo-Controlled, 3- to 8-Week, Fixed- or Flexible-Dose Studies in Adult Subjects With Schizophrenia or Bipolar Mania With Oral Risperidone
 |  | RISPERDAL
 | Placebo | 1–8 mg/day | >8–16 mg/day
 | Mean change from baseline (mg/dL)
Cholesterol | N=559 | N=742 | N=156
Change from baseline | 0.6 | 6.9 | 1.8
Triglycerides | N=183 | N=307 | N=123
Change from baseline | -17.4 | -4.9 | -8.3
 | Proportion of patients With Shifts
Cholesterol | 2.7% | 4.3% | 6.3%
(<200 mg/dL to ≥240 mg/dL) | (10/368) | (22/516) | (6/96)
Triglycerides | 1.1% | 2.7% | 2.5%
(<500 mg/dL to ≥500 mg/dL) | (2/180) | (8/301) | (3/121)

In longer-term, controlled and uncontrolled studies, RISPERDAL was associated with a mean change in (a) non-fasting cholesterol of +4.4 mg/dL at Week 24 (N=231) and +5.5 mg/dL at Week 48 (N=86); and (b) non-fasting triglycerides of +19.9 mg/dL at Week 24 (N=52).

Weight Gain

Weight gain has been observed with atypical antipsychotic use. Clinical monitoring of weight is recommended.

Data from a placebo-controlled, 12-week, fixed-dose study in adult subjects with schizophrenia are presented in Table 3.

Table 3. Mean Change in Body Weight (kg) and the Proportion of Subjects With ≥7% Gain in Body Weight From a Placebo-Controlled, 12-Week, Fixed-Dose Study in Adult Subjects With Schizophrenia
 |  | RISPERDAL CONSTA
 | Placebo (N=83) | 25 mg (N=90) | 50 mg (N=87)
Weight (kg)
Change from baseline | -1.4 | 0.5 | 1.2
Weight Gain
≥7% increase from baseline | 6% | 10% | 8%

In an uncontrolled, longer-term, open-label study, RISPERDAL CONSTA was associated with a mean change in weight of +2.1 kg at Week 24 (N=268) and +2.8 kg at Week 50 (N=199).

5.6 Hyperprolactinemia

As with other drugs that antagonize dopamine D2receptors, risperidone elevates prolactin levels and the elevation persists during chronic administration. Risperidone is associated with higher levels of prolactin elevation than other antipsychotic agents.

Hyperprolactinemia may suppress hypothalamic GnRH, resulting in reduced pituitary gonadotropin secretion. This, in turn, may inhibit reproductive function by impairing gonadal steroidogenesis in both female and male patients. Galactorrhea, amenorrhea, gynecomastia, and impotence have been reported in patients receiving prolactin-elevating compounds. Long-standing hyperprolactinemia when associated with hypogonadism may lead to decreased bone density in both female and male subjects.

Tissue culture experiments indicate that approximately one-third of human breast cancers are prolactin dependent in vitro, a factor of potential importance if the prescription of these drugs is contemplated in a patient with previously detected breast cancer. An increase in pituitary gland, mammary gland, and pancreatic islet cell neoplasia (mammary adenocarcinomas, pituitary and pancreatic adenomas) was observed in the risperidone carcinogenicity studies conducted in mice and rats [see Nonclinical Toxicology (13.1)] . Published epidemiologic studies have shown inconsistent results when exploring the potential association between hyperprolactinemia and breast cancer.

5.7 Orthostatic Hypotension

RISPERDAL CONSTA may induce orthostatic hypotension associated with dizziness, tachycardia, and in some patients, syncope, especially during the initial dose-titration period with oral risperidone, probably reflecting its alpha-adrenergic antagonistic properties. Syncope was reported in 0.8% (12/1499 patients) of patients treated with RISPERDAL CONSTA in multiple-dose studies. Patients should be instructed in nonpharmacologic interventions that help to reduce the occurrence of orthostatic hypotension (e.g., sitting on the edge of the bed for several minutes before attempting to stand in the morning and slowly rising from a seated position).

RISPERDAL CONSTA should be used with particular caution in (1) patients with known cardiovascular disease (history of myocardial infarction or ischemia, heart failure, or conduction abnormalities), cerebrovascular disease, and conditions which would predispose patients to hypotension, e.g., dehydration and hypovolemia, and (2) in the elderly and patients with renal or hepatic impairment. Monitoring of orthostatic vital signs should be considered in all such patients, and a dose reduction should be considered if hypotension occurs. Clinically significant hypotension has been observed with concomitant use of oral RISPERDAL and antihypertensive medication.

5.8 Falls

Somnolence, postural hypotension, motor and sensory instability have been reported with the use of antipsychotics, including RISPERDAL CONSTA, which may lead to falls and, consequently, fractures or other fall-related injuries. For patients, particularly the elderly, with diseases, conditions, or medications that could exacerbate these effects, assess the risk of falls when initiating antipsychotic treatment and recurrently for patients on long-term antipsychotic therapy.

5.9 Leukopenia, Neutropenia, and Agranulocytosis

Class Effect: In clinical trial and/or postmarketing experience, events of leukopenia/neutropenia have been reported temporally related to antipsychotic agents, including RISPERDAL CONSTA. Agranulocytosis has also been reported.

Possible risk factors for leukopenia/neutropenia include pre-existing low white blood cell count (WBC) and a history of drug-induced leukopenia/neutropenia. Patients with a history of a clinically significant low WBC or a drug-induced leukopenia/neutropenia should have their complete blood count (CBC) monitored frequently during the first few months of therapy and discontinuation of RISPERDAL CONSTA should be considered at the first sign of a clinically significant decline in WBC in the absence of other causative factors.

Patients with clinically significant neutropenia should be carefully monitored for fever or other symptoms or signs of infection and treated promptly if such symptoms or signs occur. Patients with severe neutropenia (absolute neutrophil count <1000/mm^3) should discontinue RISPERDAL CONSTA and have their WBC followed until recovery.

5.10 Potential for Cognitive and Motor Impairment

Somnolence was reported by 5% of patients treated with RISPERDAL CONSTA in multiple-dose trials. Since risperidone has the potential to impair judgment, thinking, or motor skills, patients should be cautioned about operating hazardous machinery, including automobiles, until they are reasonably certain that treatment with RISPERDAL CONSTA does not affect them adversely.

5.11 Seizures

During premarketing testing, seizures occurred in 0.3% (5/1499 patients) of patients treated with RISPERDAL CONSTA. Therefore, RISPERDAL CONSTA should be used cautiously in patients with a history of seizures.

5.12 Dysphagia

Esophageal dysmotility and aspiration have been associated with antipsychotic drug use. Aspiration pneumonia is a common cause of morbidity and mortality in patients with advanced Alzheimer's dementia. RISPERDAL CONSTA and other antipsychotic drugs should be used cautiously in patients at risk for aspiration pneumonia. [see also Boxed Warningand Warnings and Precautions (5.1)]

5.13 Priapism

Priapism has been reported during postmarketing surveillance [see Adverse Reactions (6.2)] . Severe priapism may require surgical intervention.

5.14 Body Temperature Regulation

Disruption of body temperature regulation has been attributed to antipsychotic agents. Both hyperthermia and hypothermia have been reported in association with oral RISPERDAL or RISPERDAL CONSTA use. Caution is advised when prescribing RISPERDAL CONSTA for patients who will be exposed to temperature extremes.

5.15 Administration

RISPERDAL CONSTA should be injected into the deltoid or gluteal muscle, and care must be taken to avoid inadvertent injection into a blood vessel. [see Dosage and Administration (2)and Adverse Reactions (6)] .

5.16 Osteodystrophy and Tumors in Animals

RISPERDAL CONSTA produced osteodystrophy in male and female rats in a 1-year toxicity study and a 2-year carcinogenicity study at a dose of 40 mg/kg administered IM every 2 weeks.

RISPERDAL CONSTA produced renal tubular tumors (adenoma, adenocarcinoma) and adrenomedullary pheochromocytomas in male rats in the 2-year carcinogenicity study at 40 mg/kg administered IM every 2 weeks. In addition, RISPERDAL CONSTA produced an increase in a marker of cellular proliferation in renal tissue in males in the 1-year toxicity study and in renal tumor-bearing males in the 2-year carcinogenicity study at 40 mg/kg administered IM every 2 weeks. (Cellular proliferation was not measured at the low dose or in females in either study.)

The effect dose for osteodystrophy and the tumor findings is 8 times the IM maximum recommended human dose (MRHD) (50 mg) on a mg/m^2basis and is associated with a plasma exposure (AUC) 2 times the expected plasma exposure (AUC) at the IM MRHD. The no-effect dose for these findings was 5 mg/kg (equal to the IM MRHD on a mg/m^2basis). Plasma exposure (AUC) at the no-effect dose was one third the expected plasma exposure (AUC) at the IM MRHD.

Neither the renal or adrenal tumors, nor osteodystrophy, were seen in studies of orally administered risperidone.Osteodystrophy was not observed in dogs at doses up to 14 times (based on AUC) the IM MRHD in a 1-year toxicity study.

The renal tubular and adrenomedullary tumors in male rats and other tumor findings are described in more detail in Section 13.1 (Carcinogenicity, Mutagenesis, Impairment of Fertility).

The relevance of these findings to human risk is unknown.

6 ADVERSE REACTIONS

The following are discussed in more detail in other sections of the labeling:

- Increased mortality in elderly patients with dementia-related psychosis [see Boxed Warningand Warnings and Precautions (5.1)]
- Cerebrovascular adverse events, including stroke, in elderly patients with dementia-related psychosis [see Warnings and Precautions (5.2)]
- Neuroleptic malignant syndrome [see Warnings and Precautions (5.3)]
- Tardive dyskinesia [see Warnings and Precautions (5.4)]
- Metabolic changes [see Warnings and Precautions (5.5)]
- Hyperprolactinemia [see Warnings and Precautions (5.6)]
- Orthostatic hypotension [see Warnings and Precautions (5.7)]
- Falls [see Warnings and Precautions (5.8)]
- Leukopenia/Neutropenia and Agranulocytosis [see Warnings and Precautions (5.9)]
- Potential for cognitive and motor impairment [see Warnings and Precautions (5.10)]
- Seizures [see Warnings and Precautions (5.11)]
- Dysphagia [see Warnings and Precautions (5.12)]
- Priapism [see Warnings and Precautions (5.13)]
- Disruption of body temperature regulation [see Warnings and Precautions (5.14)]
- Avoidance of inadvertent injection into a blood vessel [see Warnings and Precautions (5.15)]
- Osteodystrophy and tumors in animals [see Warnings and Precautions (5.16)]

The most common adverse reactions in clinical trials in patients with schizophrenia (≥ 5%) were: headache, parkinsonism, dizziness, akathisia, fatigue, constipation, dyspepsia, sedation, weight increased, pain in extremity, and dry mouth. The most common adverse reactions in the double-blind, placebo-controlled periods of the bipolar disorder trials were weight increased (5% in the monotherapy trial) and tremor and parkinsonism (≥ 10% in the adjunctive treatment trial).

The most common adverse reactions that were associated with discontinuation from the 12-week double-blind, placebo-controlled trial in patients with schizophrenia (causing discontinuation in ≥1% of patients) were agitation, depression, anxiety, and akathisia. Adverse reactions that were associated with discontinuation from the double-blind, placebo-controlled periods of the bipolar disorder trials were hyperglycemia (one patient in the monotherapy trial) and hypokinesia and tardive dyskinesia (one patient each in the adjunctive treatment trial).

The data described in this section are derived from a clinical trial database consisting of 2392 patients exposed to one or more doses of RISPERDAL CONSTA for the treatment of schizophrenia. Of these 2392 patients, 332 were patients who received RISPERDAL CONSTA while participating in a 12-week double-blind, placebo-controlled trial. Two hundred two (202) of the 332 were schizophrenia patients who received 25 mg or 50 mg RISPERDAL CONSTA. The conditions and duration of treatment with RISPERDAL CONSTA in the other clinical trials varied greatly and included (in overlapping categories) double-blind, fixed- and flexible-dose, placebo- or active-controlled studies and open-label phases of studies, inpatients and outpatients, and short-term (up to 12 weeks) and longer-term (up to 4 years) exposures. Safety was assessed by collecting adverse events and performing physical examinations, vital signs, body weights, laboratory analyses, and ECGs.

In addition to the studies in patients with schizophrenia, safety data are presented from a trial assessing the efficacy and safety of RISPERDAL CONSTA when administered as monotherapy for maintenance treatment in patients with bipolar I disorder. The subjects in this multi-center, double-blind, placebo-controlled study were adult patients who met DSM-IV criteria for Bipolar Disorder Type I and who were stable on risperidone (oral or long-acting injection), were stable on other antipsychotics or mood stabilizers, or were experiencing an acute episode. After a 3-week period of treatment with open-label oral risperidone (N=440), subjects who demonstrated an initial response to oral risperidone in this period and those who were stable on risperidone (oral or long-acting injection) at study entry entered into a 26-week stabilization period of open-label RISPERDAL CONSTA (N=501). Subjects who demonstrated a maintained response during this period were then randomized into a 24-month double-blind, placebo-controlled period in which they received RISPERDAL CONSTA (N=154) or placebo (N=149) as monotherapy. Subjects who relapsed or who completed the double-blind period could choose to enter an 8-week open-label RISPERDAL CONSTA extension period (N=160).

Safety data are also presented from a trial assessing the efficacy and safety of RISPERDAL CONSTA when administered as adjunctive maintenance treatment in patients with bipolar disorder. The subjects in this multi-center, double-blind, placebo-controlled study were adult patients who met DSM-IV criteria for Bipolar Disorder Type I or Type II and who experienced at least 4 episodes of mood disorder requiring psychiatric/clinical intervention in the previous 12 months, including at least 2 episodes in the 6 months prior to the start of the study. At the start of this study, all patients (N=275) entered into a 16-week open-label treatment phase in which they received RISPERDAL CONSTA in addition to continuing their treatment as usual, which consisted of various mood stabilizers (primarily lithium and valproate), antidepressants, and/or anxiolytics. Patients who reached remission at the end of this 16-week open-label treatment phase (N=139) were then randomized into a 52-week double-blind, placebo-controlled phase in which they received RISPERDAL CONSTA (N=72) or placebo (n=67) as adjunctive treatment in addition to continuing their treatment as usual. Patients who did not reach remission at the end of the 16-week open-label treatment phase could choose to continue to receive RISPERDAL CONSTA as adjunctive therapy in an open-label manner, in addition to continuing their treatment as usual, for up to an additional 36 weeks as clinically indicated for a total period of up to 52 weeks; these patients (N=70) were also included in the evaluation of safety.

Adverse events during exposure to study treatment were obtained by general inquiry and recorded by clinical investigators using their own terminology. Consequently, to provide a meaningful estimate of the proportion of individuals experiencing adverse events, events were grouped in standardized categories using MedDRA terminology.

Throughout this section, adverse reactions are reported. Adverse reactions are adverse events that were considered to be reasonably associated with the use of RISPERDAL CONSTA (adverse drug reactions) based on the comprehensive assessment of the available adverse event information. A causal association for RISPERDAL CONSTA often cannot be reliably established in individual cases. Further, because clinical trials are conducted under widely varying conditions, adverse reaction rates observed in the clinical trials of a drug cannot be directly compared to rates in the clinical trials of another drug and may not reflect the rates observed in clinical practice.

The majority of all adverse reactions were mild to moderate in severity.

6.1 Clinical Trials Experience

Commonly-Observed Adverse Reactions in Double-Blind, Placebo-Controlled Clinical Trials - Schizophrenia

Table 4 lists the adverse reactions reported in 2% or more of RISPERDAL CONSTA-treated patients with schizophrenia in one 12-week double-blind, placebo-controlled trial.

Table 4. Adverse Reactions in ≥2% of RISPERDAL CONSTA-Treated Patients with Schizophrenia in a 12-Week Double-Blind, Placebo-Controlled Trial
 | Percentage of Patients Reporting Event
 | RISPERDAL CONSTA |  | Placebo
System/Organ Class | 25 mg | 50 mg
Adverse Reaction | (N=99) | (N=103) | (N=98)
Eye disorders
Vision blurred | 2 | 3 | 0
Gastrointestinal disorders
Constipation | 5 | 7 | 1
Dry mouth | 0 | 7 | 1
Dyspepsia | 6 | 6 | 0
Nausea | 3 | 4 | 5
Toothache | 1 | 3 | 0
Salivary hypersecretion | 4 | 1 | 0
General disorders and administration site conditions
Fatigue [Fatigue includes fatigue and asthenia. Parkinsonism includes extrapyramidal disorder, musculoskeletal stiffness, muscle rigidity, and bradykinesia. Akathisia includes akathisia and restlessness. Sedation includes sedation and somnolence.] | 3 | 9 | 0
Edema peripheral | 2 | 3 | 1
Pain | 4 | 1 | 0
Pyrexia | 2 | 1 | 0
Infections and infestations
Upper respiratory tract infection | 2 | 0 | 1
Investigations
Weight increased | 5 | 4 | 2
Weight decreased | 4 | 1 | 1
Musculoskeletal and connective tissue disorders
Pain in extremity | 6 | 2 | 1
Nervous system disorders
Headache | 15 | 21 | 12
Parkinsonism | 8 | 15 | 9
Dizziness | 7 | 11 | 6
Akathisia | 4 | 11 | 6
Sedation | 5 | 6 | 3
Tremor | 0 | 3 | 0
Syncope | 2 | 1 | 0
Hypoesthesia | 2 | 0 | 0
Respiratory, thoracic and mediastinal disorders
Cough | 4 | 2 | 3
Sinus congestion | 2 | 0 | 0
Skin and subcutaneous tissue disorders
Acne | 2 | 2 | 0
Dry skin | 2 | 0 | 0

Commonly-Observed Adverse Reactions in Double-Blind, Placebo-Controlled Clinical Trials – Bipolar Disorder

Table 5 lists the treatment-emergent adverse reactions reported in 2% or more of RISPERDAL CONSTA-treated patients in the 24-month double-blind, placebo-controlled treatment period of the trial assessing the efficacy and safety of RISPERDAL CONSTA when administered as monotherapy for maintenance treatment in patients with Bipolar I Disorder.

Table 5. Adverse Reactions in ≥2% of Patients with Bipolar I Disorder Treated with RISPERDAL CONSTA as Monotherapy in a 24-Month Double-Blind, Placebo-Controlled Trial
 | Percentage of Patients Reporting Event
System/Organ Class Adverse Reaction | RISPERDAL CONSTA (N=154) | Placebo (N=149)
Investigations
Weight increased | 5 | 1
Nervous system disorders
Dizziness | 3 | 1
Vascular disorders
Hypertension | 3 | 1

Table 6 lists the treatment-emergent adverse reactions reported in 4% or more of patients in the 52-week double-blind, placebo-controlled treatment phase of a trial assessing the efficacy and safety of RISPERDAL CONSTA when administered as adjunctive maintenance treatment in patients with bipolar disorder.

Table 6. Adverse Reactions in ≥ 4% of Patients with Bipolar Disorder Treated with RISPERDAL CONSTA as Adjunctive Therapy in a 52-Week Double-Blind, Placebo-Controlled Trial
 | Percentage of Patients Reporting Event
System/Organ Class Adverse Reaction | RISPERDAL CONSTA + Treatment as Usual [Patients received double-blind RISPERDAL CONSTA or placebo in addition to continuing their treatment as usual, which included mood stabilizers, antidepressants, and/or anxiolytics.] (N=72) | Placebo + Treatment as Usual (N=67)
General disorders and administration site conditions
Gait abnormal | 4 | 0
Infections and infestations
Upper respiratory tract infection | 6 | 3
Investigations
Weight increased | 7 | 1
Metabolism and nutrition disorders
Decreased appetite | 6 | 1
Increased appetite | 4 | 0
Musculoskeletal and connective tissue disorders
Arthralgia | 4 | 3
Nervous system disorders
Tremor | 24 | 16
Parkinsonism [Parkinsonism includes muscle rigidity, hypokinesia, cogwheel rigidity, and bradykinesia. Dyskinesia includes muscle twitching and dyskinesia.] | 15 | 6
Dyskinesia | 6 | 3
Sedation [Sedation includes sedation and somnolence.] | 7 | 1
Disturbance in attention | 4 | 0
Reproductive system and breast disorders
Amenorrhea | 4 | 1
Respiratory, thoracic and mediastinal disorders
Cough | 4 | 1

Other Adverse Reactions Observed During the Clinical Trial Evaluation of Risperidone

The following additional adverse reactions occurred in < 2% of the RISPERDAL CONSTA-treated patients in the above schizophrenia double-blind, placebo-controlled trial dataset, in < 2% of the RISPERDAL CONSTA-treated patients in the above double-blind, placebo-controlled period of the monotherapy bipolar disorder trial dataset, or in < 4% of the RISPERDAL CONSTA-treated patients in the above double-blind, placebo-controlled period of the adjunctive treatment bipolar disorder trial dataset. The following also includes additional adverse reactions reported at any frequency in RISPERDAL CONSTA-treated patients who participated in the open-label phases of the above bipolar disorder studies and in other studies, including double-blind, active controlled and open-label studies in schizophrenia and bipolar disorder.

Blood and lymphatic system disorders:anemia, neutropenia

Cardiac disorders:tachycardia, atrioventricular block first degree, palpitations, sinus bradycardia, bundle branch block left, bradycardia, sinus tachycardia, bundle branch block right

Ear and labyrinth disorders:ear pain, vertigo

Endocrine disorders:hyperprolactinemia

Eye disorders:conjunctivitis, visual acuity reduced

Gastrointestinal disorders:diarrhea, vomiting, abdominal pain upper, abdominal pain, stomach discomfort, gastritis

General disorders and administration site conditions:injection site pain, chest discomfort, chest pain, influenza like illness, sluggishness, malaise, induration, injection site induration, injection site swelling, injection site reaction, face edema

Immune system disorders:hypersensitivity

Infections and infestations:nasopharyngitis, influenza, bronchitis, urinary tract infection, rhinitis, respiratory tract infection, ear infection, pneumonia, lower respiratory tract infection, pharyngitis, sinusitis, viral infection, infection, localized infection, cystitis, gastroenteritis, subcutaneous abscess

Injury and poisoning:fall, procedural pain

Investigations:blood prolactin increased, alanine aminotransferase increased, electrocardiogram abnormal, gamma-glutamyl transferase increased, blood glucose increased, hepatic enzyme increased, aspartate aminotransferase increased, electrocardiogram QT prolonged, glucose urine present

Metabolism and nutritional disorders:anorexia, hyperglycemia

Musculoskeletal, connective tissue and bone disorders:posture abnormal, myalgia, back pain, buttock pain, muscular weakness, neck pain, musculoskeletal chest pain

Nervous system disorders:coordination abnormal, dystonia, tardive dyskinesia, drooling, paresthesia, dizziness postural, convulsion, akinesia, hypokinesia, dysarthria

Psychiatric disorders:insomnia, agitation, anxiety, sleep disorder, depression, initial insomnia, libido decreased, nervousness

Renal and urinary disorders:urinary incontinence

Reproductive system and breast disorders:galactorrhea, oligomenorrhea, erectile dysfunction, sexual dysfunction, ejaculation disorder, gynecomastia, breast discomfort, menstruation irregular, menstruation delayed, menstrual disorder, ejaculation delayed

Respiratory, thoracic and mediastinal disorders:nasal congestion, pharyngolaryngeal pain, dyspnea, rhinorrhea

Skin and subcutaneous tissue disorders:rash, eczema, pruritus generalized, pruritus

Vascular disorders:hypotension, orthostatic hypotension

Additional Adverse Reactions Reported with Oral RISPERDAL

The following is a list of additional adverse reactions that have been reported during the clinical trial evaluation of oral RISPERDAL, regardless of frequency of occurrence:

Blood and Lymphatic Disorders:granulocytopenia

Cardiac Disorders:atrioventricular block

Ear and Labyrinth Disorders:tinnitus

Eye Disorders:ocular hyperemia, eye discharge, eye rolling, eyelid edema, eye swelling, eyelid margin crusting, dry eye, lacrimation increased, photophobia, glaucoma

Gastrointestinal Disorders:abdominal pain upper, dysphagia, fecaloma, abdominal discomfort, fecal incontinence, lip swelling, cheilitis, aptyalism

General Disorders:thirst, feeling abnormal, gait disturbance, pitting edema, edema, chills, discomfort, generalized edema, drug withdrawal syndrome, peripheral coldness

Immune System Disorders:drug hypersensitivity

Infections and Infestations:tonsillitis, eye infection, cellulitis, otitis media, onychomycosis, acarodermatitis, bronchopneumonia, respiratory tract infection, tracheobronchitis, otitis media chronic

Investigations:body temperature increased, heart rate increased, eosinophil count increased, white blood cell count decreased, hemoglobin decreased, blood creatine phosphokinase increased, hematocrit decreased, body temperature decreased, blood pressure decreased, transaminases increased

Metabolism and Nutrition Disorders:polydipsia

Musculoskeletal, Connective Tissue, and Bone Disorders:joint swelling, joint stiffness, rhabdomyolysis, torticollis

Nervous System Disorders:hypertonia, balance disorder, dysarthria, unresponsive to stimuli, depressed level of consciousness, movement disorder, hypokinesia, parkinsonian rest tremor, transient ischemic attack, cerebrovascular accident, masked facies, speech disorder, loss of consciousness, muscle contractions involuntary, akinesia, cerebral ischemia, cerebrovascular disorder, neuroleptic malignant syndrome, diabetic coma, head titubation

Psychiatric Disorders:blunted affect, confusional state, middle insomnia, listlessness, anorgasmia

Renal and Urinary Disorders:enuresis, dysuria, pollakiuria

Reproductive System and Breast Disorders:vaginal discharge, retrograde ejaculation, ejaculation disorder, ejaculation failure, breast enlargement

Respiratory, Thoracic, and Mediastinal Disorders:epistaxis, wheezing, pneumonia aspiration, dysphonia, productive cough, pulmonary congestion, respiratory tract congestion, rales, respiratory disorder, hyperventilation, nasal edema

Skin and Subcutaneous Tissue Disorders:erythema, skin discoloration, skin lesion, skin disorder, rash erythematous, rash papular, hyperkeratosis, dandruff, seborrheic dermatitis, rash generalized, rash maculopapular

Vascular Disorders:flushing

Discontinuations Due to Adverse Reactions

Schizophrenia

Approximately 11% (22/202) of RISPERDAL CONSTA-treated patients in the 12-week double-blind, placebo-controlled schizophrenia trial discontinued treatment due to an adverse event, compared with 13% (13/98) who received placebo. The adverse reactions associated with discontinuation in two or more RISPERDAL CONSTA-treated patients were: agitation (3%), depression (2%), anxiety (1%), and akathisia (1%).

Bipolar Disorder

In the 24-month double-blind, placebo-controlled treatment period of the trial assessing the efficacy and safety of RISPERDAL CONSTA when administered as monotherapy for maintenance treatment in patients with bipolar I disorder, 1 (0.6%) of 154 RISPERDAL CONSTA-treated patients discontinued due to an adverse reaction (hyperglycemia).

In the 52-week double-blind phase of the placebo-controlled trial in which RISPERDAL CONSTA was administered as adjunctive therapy to patients with bipolar disorder in addition to continuing with their treatment as usual, approximately 4% (3/72) of RISPERDAL CONSTA-treated patients discontinued treatment due to an adverse event, compared with 1.5% (1/67) of placebo-treated patients. Adverse reactions associated with discontinuation in RISPERDAL CONSTA-treated patients were: hypokinesia (one patient) and tardive dyskinesia (one patient).

Dose Dependency of Adverse Reactions in Clinical Trials

Extrapyramidal Symptoms

Two methods were used to measure extrapyramidal symptoms (EPS) in the 12-week double-blind, placebo-controlled trial comparing three doses of RISPERDAL CONSTA (25 mg, 50 mg, and 75 mg) with placebo in patients with schizophrenia, including: (1) the incidence of spontaneous reports of EPS symptoms; and (2) the change from baseline to endpoint on the total score (sum of the subscale scores for parkinsonism, dystonia, and dyskinesia) of the Extrapyramidal Symptom Rating Scale (ESRS).

As shown in Table 1, the overall incidence of EPS-related adverse reactions (akathisia, dystonia, parkinsonism, and tremor) in patients treated with 25 mg RISPERDAL CONSTA was comparable to that of patients treated with placebo; the incidence of EPS-related adverse reactions was higher in patients treated with 50 mg RISPERDAL CONSTA.

The median change from baseline to endpoint in total ESRS score showed no worsening in patients treated with RISPERDAL CONSTA compared with patients treated with placebo: 0 (placebo group); -1 (25-mg group, significantly less than the placebo group); and 0 (50-mg group).

Dystonia

Class Effect:Symptoms of dystonia, prolonged abnormal contractions of muscle groups, may occur in susceptible individuals during the first few days of treatment. Dystonic symptoms include: spasm of the neck muscles, sometimes progressing to tightness of the throat, swallowing difficulty, difficulty breathing, and/or protrusion of the tongue. While these symptoms can occur at low doses, they occur more frequently and with greater severity with high potency and at higher doses of first generation antipsychotic drugs. An elevated risk of acute dystonia is observed in males and younger age groups.

Changes in ECG

The electrocardiograms of 202 schizophrenic patients treated with 25 mg or 50 mg RISPERDAL CONSTA and 98 schizophrenic patients treated with placebo in the 12-week double-blind, placebo-controlled trial were evaluated. Compared with placebo, there were no statistically significant differences in QTc intervals (using Fridericia's and linear correction factors) during treatment with RISPERDAL CONSTA.

The electrocardiograms of 227 patients with Bipolar I Disorder were evaluated in the 24-month double-blind, placebo-controlled period. There were no clinically relevant differences in QTc intervals (using Fridericia's and linear correction factors) during treatment with RISPERDAL CONSTA compared to placebo.

The electrocardiograms of 85 patients with bipolar disorder were evaluated in the 52-week double-blind, placebo-controlled trial. There were no statistically significant differences in QTc intervals (using Fridericia's and linear correction factors) during treatment with RISPERDAL CONSTA 25 mg, 37.5 mg, or 50 mg when administered as adjunctive treatment in addition to continuing treatment as usual compared to placebo.

Pain Assessment and Local Injection Site Reactions

The mean intensity of injection pain reported by patients with schizophrenia using a visual analog scale (0 = no pain to 100 = unbearably painful) decreased in all treatment groups from the first to the last injection (placebo: 16.7 to 12.6; 25 mg: 12.0 to 9.0; 50 mg: 18.2 to 11.8). After the sixth injection (Week 10), investigator ratings indicated that 1% of patients treated with 25 mg or 50 mg RISPERDAL CONSTA experienced redness, swelling, or induration at the injection site.

In a separate study to observe local-site tolerability in which RISPERDAL CONSTA was administered into the deltoid muscle every 2 weeks over a period of 8 weeks, no patient discontinued treatment due to local injection site pain or reaction. Clinician ratings indicated that only mild redness, swelling, or induration at the injection site was observed in subjects treated with 37.5 mg or 50 mg RISPERDAL CONSTA at 2 hours after deltoid injection. All ratings returned to baseline at the predose assessment of the next injection 2 weeks later. No moderate or severe reactions were observed in any subject.

6.2 Postmarketing Experience

The following adverse reactions have been identified during postapproval use of risperidone; because these reactions are reported voluntarily from a population of uncertain size, it is not possible to reliably estimate their frequency: agranulocytosis, alopecia, anaphylactic reaction, angioedema, atrial fibrillation, blood cholesterol increased, blood triglycerides increased, catatonia, diabetes mellitus, diabetic ketoacidosis in patients with impaired glucose metabolism, drug withdrawal syndrome neonatal, dysgeusia, hypoglycemia, hypothermia, ileus, inappropriate antidiuretic hormone secretion, intestinal obstruction, jaundice, mania, pancreatitis, priapism, QT prolongation, sleep apnea syndrome, somnambulism, Stevens-Johnson syndrome and toxic epidermal necrolysis (SJS/TEN), thrombocytopenia, thrombotic thrombocytopenic purpura, urinary retention, and water intoxication. In addition, the following adverse reactions have been observed during postapproval use of RISPERDAL CONSTA: cerebrovascular disorders, including cerebrovascular accidents, and diabetes mellitus aggravated.

Retinal artery occlusion after injection of RISPERDAL CONSTA has been reported during postmarketing surveillance. This has been reported in the presence of abnormal arteriovenous anastomosis.

Serious injection site reactions including abscess, cellulitis, cyst, hematoma, necrosis, nodule, and ulcer have been reported with RISPERDAL CONSTA during postmarketing surveillance. Isolated cases required surgical intervention.

Very rarely, cases of anaphylactic reaction after injection with RISPERDAL CONSTA have been reported during postmarketing experience in patients who have previously tolerated oral risperidone.

Postmarketing cases of extrapyramidal symptoms (dystonia and dyskinesia) have been reported in patients concomitantly taking methylphenidate and risperidone when there was an increase or decrease in dosage, initiation, or discontinuation of either or both medications.

7 DRUG INTERACTIONS

The interactions of RISPERDAL CONSTA with coadministration of other drugs have not been systematically evaluated. The drug interaction data provided in this section is based on studies with oral RISPERDAL.

7.1 Centrally-Acting Drugs and Alcohol

Given the primary CNS effects of risperidone, caution should be used when RISPERDAL CONSTA is administered in combination with other centrally-acting drugs or alcohol.

7.2 Drugs with Hypotensive Effects

Because of its potential for inducing hypotension, RISPERDAL CONSTA may enhance the hypotensive effects of other therapeutic agents with this potential.

7.3 Levodopa and Dopamine Agonists

RISPERDAL CONSTA may antagonize the effects of levodopa and dopamine agonists.

7.4 Amitriptyline

Amitriptyline did not affect the pharmacokinetics of risperidone or of risperidone and 9-hydroxyrisperidone combined following concomitant administration with oral RISPERDAL.

7.5 Cimetidine and Ranitidine

Cimetidine and ranitidine increased the bioavailability of oral risperidone by 64% and 26%, respectively. However, cimetidine did not affect the AUC of risperidone and 9-hydroxyrisperidone combined, whereas ranitidine increased the AUC of risperidone and 9-hydroxyrisperidone combined by 20%.

7.6 Methylphenidate

Concomitant use with methylphenidate, when there is change in dosage of either medication, may increase the risk of extrapyramidal symptoms (EPS). Monitor for symptoms of EPS with concomitant use of RISPERDAL CONSTA and methylphenidate [see Adverse Reactions (6.2)] .

7.7 Clozapine

Chronic administration of clozapine with risperidone may decrease the clearance of risperidone.

7.8 Lithium

Repeated doses of oral RISPERDAL (3 mg twice daily) did not affect the exposure (AUC) or peak plasma concentrations (Cmax) of lithium (N=13).

7.9 Valproate

Repeated doses of oral RISPERDAL (4 mg once daily) did not affect the pre-dose or average plasma concentrations and exposure (AUC) of valproate (1000 mg/day in three divided doses) compared to placebo (N=21). However, there was a 20% increase in valproate peak plasma concentration (Cmax) after concomitant administration of oral RISPERDAL.

7.10 Digoxin

Oral RISPERDAL (0.25 mg twice daily) did not show a clinically relevant effect on the pharmacokinetics of digoxin.

7.11 Topiramate

Oral RISPERDAL administered at doses from 1–6 mg/day concomitantly with topiramate 400 mg/day resulted in a 23% decrease in risperidone Cmax and a 33% decrease in risperidone AUC0–12 hour at steady state. Minimal reductions in the exposure to risperidone and 9-hydroxyrisperidone combined, and no change for 9-hydroxyrisperidone were observed. This interaction is unlikely to be of clinical significance. There was no clinically relevant effect of oral RISPERDAL on the pharmacokinetics of topiramate.

7.12 Drugs That Inhibit CYP 2D6 and Other CYP Isozymes

Risperidone is metabolized to 9-hydroxyrisperidone by CYP 2D6, an enzyme that is polymorphic in the population and that can be inhibited by a variety of psychotropic and other drugs [see Clinical Pharmacology (12.3)] . Drug interactions that reduce the metabolism of risperidone to 9-hydroxyrisperidone would increase the plasma concentrations of risperidone and lower the concentrations of 9-hydroxyrisperidone. Analysis of clinical studies involving a modest number of poor metabolizers (n≅70 patients) does not suggest that poor and extensive metabolizers have different rates of adverse effects. No comparison of effectiveness in the two groups has been made.

In vitrostudies showed that drugs metabolized by other CYP isozymes, including 1A1, 1A2, 2C9, 2C19, and 3A4, are only weak inhibitors of risperidone metabolism.

Fluoxetine and Paroxetine

Fluoxetine (20 mg once daily) and paroxetine (20 mg once daily), CYP 2D6 inhibitors, have been shown to increase the plasma concentration of risperidone 2.5–2.8 fold and 3–9 fold respectively. Fluoxetine did not affect the plasma concentration of 9-hydroxyrisperidone. Paroxetine lowered the concentration of 9-hydroxyrisperidone by about 10%. When either concomitant fluoxetine or paroxetine is initiated or discontinued, the physician should re-evaluate the dose of RISPERDAL CONSTA. When initiation of fluoxetine or paroxetine is considered, patients may be placed on a lower dose of RISPERDAL CONSTA between 2 to 4 weeks before the planned start of fluoxetine or paroxetine therapy to adjust for the expected increase in plasma concentrations of risperidone. When fluoxetine or paroxetine is initiated in patients receiving the recommended dose of 25 mg RISPERDAL CONSTA, it is recommended to continue treatment with the 25-mg dose unless clinical judgment necessitates lowering the RISPERDAL CONSTA dose to 12.5 mg or necessitates interruption of RISPERDAL CONSTA treatment. When RISPERDAL CONSTA is initiated in patients already receiving fluoxetine or paroxetine, a starting dose of 12.5 mg can be considered. The efficacy of the 12.5 mg dose has not been investigated in clinical trials. [see also Dosage and Administration (2.5)] . The effects of discontinuation of concomitant fluoxetine or paroxetine therapy on the pharmacokinetics of risperidone and 9-hydroxyrisperidone have not been studied.

Erythromycin

There were no significant interactions between oral RISPERDAL and erythromycin.

7.13 Carbamazepine and Other CYP 3A4 Enzyme Inducers

Carbamazepine co-administration with oral RISPERDAL decreased the steady-state plasma concentrations of risperidone and 9-hydroxyrisperidone by about 50%. Plasma concentrations of carbamazepine did not appear to be affected. Co-administration of other known CYP 3A4 enzyme inducers (e.g., phenytoin, rifampin, and phenobarbital) with risperidone may cause similar decreases in the combined plasma concentrations of risperidone and 9-hydroxyrisperidone, which could lead to decreased efficacy of RISPERDAL CONSTA treatment. At the initiation of therapy with carbamazepine or other known hepatic enzyme inducers, patients should be closely monitored during the first 4–8 weeks, since the dose of RISPERDAL CONSTA may need to be adjusted. A dose increase, or additional oral RISPERDAL, may need to be considered. On discontinuation of carbamazepine or other CYP 3A4 hepatic enzyme inducers, the dosage of RISPERDAL CONSTA should be re-evaluated and, if necessary, decreased. Patients may be placed on a lower dose of RISPERDAL CONSTA between 2 to 4 weeks before the planned discontinuation of carbamazepine or other CYP 3A4 enzyme inducers to adjust for the expected increase in plasma concentrations of risperidone plus 9-hydroxyrisperidone. For patients treated with the recommended dose of 25 mg RISPERDAL CONSTA and discontinuing from carbamazepine or other CYP 3A4 enzyme inducers, it is recommended to continue treatment with the 25-mg dose unless clinical judgment necessitates lowering the RISPERDAL CONSTA dose to 12.5 mg or necessitates interruption of RISPERDAL CONSTA treatment. The efficacy of the 12.5 mg dose has not been investigated in clinical trials. [see also Dosage and Administration (2.5)]

7.14 Drugs Metabolized by CYP 2D6

In vitrostudies indicate that risperidone is a relatively weak inhibitor of CYP 2D6. Therefore, RISPERDAL CONSTA is not expected to substantially inhibit the clearance of drugs that are metabolized by this enzymatic pathway. In drug interaction studies, oral RISPERDAL did not significantly affect the pharmacokinetics of donepezil and galantamine, which are metabolized by CYP 2D6.

8 USE IN SPECIFIC POPULATIONS

8.1 Pregnancy

Pregnancy Exposure Registry

There is a pregnancy exposure registry that monitors pregnancy outcomes in women exposed to atypical antipsychotics, including RISPERDAL CONSTA, during pregnancy. Healthcare providers are encouraged to register patients by contacting the National Pregnancy Registry for Atypical Antipsychotics at 1-866-961-2388 or online at http://womensmentalhealth.org/clinical-and-research-programs/pregnancyregistry/.

Risk Summary

Neonates exposed to antipsychotic drugs during the third trimester of pregnancy are at risk for extrapyramidal and/or withdrawal symptoms following delivery (see Clinical Considerations) . Overall, available data from published epidemiologic studies of pregnant women exposed to risperidone have not established a drug-associated risk of major birth defects, miscarriage, or adverse maternal or fetal outcomes (see Data). There are risks to the mother associated with untreated schizophrenia or bipolar I disorder and with exposure to antipsychotics, including RISPERDAL CONSTA, during pregnancy (see Clinical Considerations) . Risperidone has been detected in plasma in adult subjects up to 8 weeks after a single-dose administration of RISPERDAL CONSTA [see Clinical Pharmacology (12.3)] . The clinical significance of RISPERDAL CONSTA administered before pregnancy or anytime during pregnancy is not known.

Oral administration of risperidone to pregnant mice caused cleft palate at doses 3 to 4 times the maximum recommended human dose (MRHD) with maternal toxicity observed at 4-times the MRHD based on mg/m^2 body surface area. Risperidone was not teratogenic in rats or rabbits at doses up to 6-times the MRHD based on mg/m^2 body surface area. Increased stillbirths and decreased birth weight occurred after oral risperidone administration to pregnant rats at 1.5-times the MRHD based on mg/m^2 body surface area. Learning was impaired in offspring of rats when the dams were dosed at 0.6-times the MRHD and offspring mortality increased at doses 0.1 to 3 times the MRHD based on mg/m^2 body surface area.

The estimated background risk of major birth defects and miscarriage for the indicated population is unknown. All pregnancies have a background risk of birth defect, loss, or other adverse outcomes. In the U.S. general population, the estimated background risk of major birth defects and miscarriage in clinically recognized pregnancies is 2–4% and 15–20%, respectively.

Clinical Considerations

Disease-associated Maternal and/or Embryo/Fetal Risk

There is a risk to the mother from untreated schizophrenia or bipolar I disorder, including increased risk of relapse, hospitalization, and suicide. Schizophrenia and bipolar I disorder are associated with increased adverse perinatal outcomes, including preterm birth. It is not known if this is a direct result of the illness or other comorbid factors.

Fetal/Neonatal Adverse Reactions

Extrapyramidal and/or withdrawal symptoms, including agitation, hypertonia, hypotonia, tremor, somnolence, respiratory distress, and feeding disorder have been reported in neonates who were exposed to antipsychotic drugs, including RISPERDAL CONSTA, during the third trimester of pregnancy. These symptoms have varied in severity. Monitor neonates for extrapyramidal and/or withdrawal symptoms and manage symptoms appropriately. Some neonates recovered within hours or days without specific treatment; others required prolonged hospitalization.

Data

Human Data

Published data from observational studies, birth registries, and case reports on the use of atypical antipsychotics during pregnancy do not report a clear association with antipsychotics and major birth defects. A prospective observational study including 6 women treated with risperidone demonstrated placental passage of risperidone. A retrospective cohort study from a Medicaid database of 9258 women exposed to antipsychotics during pregnancy did not indicate an overall increased risk for major birth defects. There was a small increase in the risk major of birth defects (RR=1.26, 95% CI 1.02–1.56) and of cardiac malformations (RR=1.26, 95% CI 0.88–1.81) in a subgroup of 1566 women exposed to risperidone during the first trimester of pregnancy; however, there is no mechanism of action to explain the difference in malformation rates.

Animal Data

Oral administration of risperidone to pregnant mice during organogenesis caused cleft palate at 10 mg/kg/day which is 3 times the MRHD of 16 mg/day based on mg/m^2 body surface area; maternal toxicity occurred at 4 times the MRHD. Risperidone was not teratogenic when administered orally to rats at 0.6 to 10 mg/kg/day and rabbits at 0.3 to 5 mg/kg/day, which are up to 6 times the MRHD of 16 mg/day risperidone based on mg/m^2 body surface area. Learning was impaired in offspring of rats dosed orally throughout pregnancy at 1 mg/kg/day which is 0.6 times the MRHD and neuronal cell death increased in fetal brains of offspring of rats dosed during pregnancy at 1 and 2 mg/kg/day which are 0.6 and 1.2 times the MRHD based on mg/m^2 body surface area; postnatal development and growth of the offspring were also delayed.

Rat offspring mortality increased during the first 4 days of lactation when pregnant rats were dosed throughout gestation at 0.16 to 5 mg/kg/day which are 0.1 to 3 times the MRHD of 16 mg/day based on mg/m^2 body surface area. It is not known whether these deaths were due to a direct effect on the fetuses or pups or to effects on the dams; a no-effect dose could not be determined. The rate of stillbirths was increased at 2.5 mg/kg or 1.5 times the MRHD based on mg/m^2 body surface area.

In a rat cross-fostering study the number of live offspring was decreased, the number of stillbirths increased, and the birth weight was decreased in offspring of drug-treated pregnant rats. In addition, the number of deaths increased by Day 1 among offspring of drug-treated pregnant rats, regardless of whether or not the offspring were cross-fostered. Risperidone also appeared to impair maternal behavior in that offspring body weight gain and survival (from Day 1 to 4 of lactation) were reduced in offspring born to control but reared by drug-treated dams. All of these effects occurred at 5 mg/kg which is 3 times the MRHD based on mg/m^2 and the only dose tested in the study.

8.2 Lactation

Risk Summary

Limited data from published literature reports the presence of risperidone and its metabolite, 9-hydroxyrisperidone, in human breast milk at relative infant dose ranging between 2.3% and 4.7% of the maternal weight-adjusted dosage. There are reports of sedation, failure to thrive, jitteriness, and extrapyramidal symptoms (tremors and abnormal muscle movements) in breastfed infants exposed to risperidone (see Clinical Considerations). Risperidone has been detected in plasma in adult subjects up to 8 weeks after a single-dose administration of RISPERDAL CONSTA [see Clinical Pharmacology (12.3)] , and the clinical significance on the breastfed infant is not known. There is no information on the effects of risperidone on milk production. The developmental and health benefits of breastfeeding should be considered along with the mother's clinical need for RISPERDAL CONSTA and any potential adverse effects on the breastfed child from RISPERDAL CONSTA or from the mother's underlying condition.

Clinical Considerations

Infants exposed to RISPERDAL CONSTA through breastmilk should be monitored for excess sedation, failure to thrive, jitteriness, and extrapyramidal symptoms (tremors and abnormal muscle movements).

8.3 Females and Males of Reproductive Potential

Infertility

Females

Based on the pharmacologic action of risperidone (D2 receptor antagonism), treatment with RISPERDAL CONSTA may result in an increase in serum prolactin levels, which may lead to a reversible reduction in fertility in females of reproductive potential [see Warnings and Precautions (5.6)].

8.4 Pediatric Use

Safety and effectiveness of RISPERDAL CONSTA in pediatric patients have not been established. However, juvenile animal toxicology studies have been conducted with oral risperidone.

Juvenile Animal Studies

Juvenile dogs were treated with oral risperidone from weeks 10 to 50 of age (equivalent to the period of childhood through adolescence in humans), at doses of 0.31, 1.25, or 5 mg/kg/day, which are 1.2, 3.4 and 13.5 times the MRHD of 6 mg/day for children, based on mg/m^2 body surface area. Bone length and density were decreased with a no-effect dose of 0.31 mg/kg/day; this dose produced plasma AUC of risperidone plus its active metabolite paliperidone (9-hydroxy-risperidone) that were similar to those in children and adolescents receiving the MRHD of 6 mg/day. In addition, sexual maturation was delayed at all doses in both males and females. The above effects showed little or no reversibility in females after a 12 week drug-free recovery period. Juvenile rats, treated with oral risperidone from days 12 to 50 of age (equivalent to the period of infancy through adolescence in humans) showed impaired learning and memory performance (reversible only in females), with a no-effect dose of 0.63 mg/kg/day which is 0.5 times the MRHD of 6 mg/day for children, based on mg/m^2body surface area. This dose produced plasma AUC of risperidone plus paliperidone about half the exposure observed in humans at the MRHD. No other consistent effects on neurobehavioral or reproductive development were seen up to the highest tested dose of 1.25 mg/kg/day which is 1 time the MRHD and produced plasma AUC of risperidone plus paliperidone that were about two thirds of those observed in humans at the MRHD of 6 mg/day for children.

8.5 Geriatric Use

In an open-label study, 57 clinically stable, elderly patients (≥ 65 years old) with schizophrenia or schizoaffective disorder received RISPERDAL CONSTA every 2 weeks for up to 12 months. In general, no differences in the tolerability of RISPERDAL CONSTA were observed between otherwise healthy elderly and nonelderly patients. Therefore, dosing recommendations for otherwise healthy elderly patients are the same as for nonelderly patients. Because elderly patients exhibit a greater tendency to orthostatic hypotension than nonelderly patients, elderly patients should be instructed in nonpharmacologic interventions that help to reduce the occurrence of orthostatic hypotension (e.g., sitting on the edge of the bed for several minutes before attempting to stand in the morning and slowly rising from a seated position). In addition, monitoring of orthostatic vital signs should be considered in elderly patients for whom orthostatic hypotension is of concern [see Warnings and Precautions (5.7)] .

Concomitant use with Furosemide in Elderly Patients with Dementia-Related Psychosis

In two of four placebo-controlled trials in elderly patients with dementia-related psychosis, a higher incidence of mortality was observed in patients treated with furosemide plus oral risperidone when compared to patients treated with oral risperidone alone or with oral placebo plus furosemide. No pathological mechanism has been identified to explain this finding, and no consistent pattern for cause of death was observed. An increase of mortality in elderly patients with dementia-related psychosis was seen with the use of oral risperidone regardless of concomitant use with furosemide. RISPERDAL CONSTA is not approved for the treatment of patients with dementia-related psychosis. [see Boxed Warningand Warnings and Precautions (5.1)] .

8.6 Renal or Hepatic Impairment

In patients with renal or hepatic impairment, carefully titrate with oral risperidone prior to initiating treatment with RISPERDAL CONSTA [see Dosage and Administration (2.4)].

Patients with renal impairment may have less ability to eliminate risperidone than patients with normal renal function. Patients with impaired hepatic function may have an increase in the free fraction of risperidone, possibly resulting in an enhanced effect [see Clinical Pharmacology (12.3)] .

8.7 Patients with Parkinson's Disease or Lewy Body Dementia

Patients with Parkinson's Disease or Dementia with Lewy Bodies can experience increased sensitivity to RISPERDAL CONSTA. Manifestations can include confusion, obtundation, postural instability with frequent falls, extrapyramidal symptoms, and clinical features consistent with neuroleptic malignant syndrome.

9 DRUG ABUSE AND DEPENDENCE

9.1 Controlled Substance

RISPERDAL CONSTA (risperidone) is not a controlled substance.

9.2 Abuse

RISPERDAL CONSTA has not been systematically studied in animals or humans for its potential for abuse. Because RISPERDAL CONSTA is to be administered by health care professionals, the potential for misuse or abuse by patients is low.

9.3 Dependence

RISPERDAL CONSTA has not been systematically studied in animals or humans for its potential for tolerance or physical dependence.

10 OVERDOSAGE

10.1 Human Experience

No cases of overdose were reported in premarketing studies with RISPERDAL CONSTA. Because RISPERDAL CONSTA is to be administered by health care professionals, the potential for overdosage by patients is low.

In premarketing experience with oral RISPERDAL, there were eight reports of acute RISPERDAL overdosage, with estimated doses ranging from 20 to 300 mg and no fatalities. In general, reported signs and symptoms were those resulting from an exaggeration of the drug's known pharmacological effects, i.e., drowsiness and sedation, tachycardia and hypotension, and extrapyramidal symptoms. One case, involving an estimated overdose of 240 mg, was associated with hyponatremia, hypokalemia, prolonged QT, and widened QRS. Another case, involving an estimated overdose of 36 mg, was associated with a seizure.

Postmarketing experience with oral RISPERDAL includes reports of acute overdose, with estimated doses of up to 360 mg. In general, the most frequently reported signs and symptoms are those resulting from an exaggeration of the drug's known pharmacological effects, i.e., drowsiness, sedation, tachycardia, hypotension, and extrapyramidal symptoms. Other adverse reactions reported since market introduction related to oral RISPERDAL overdose include prolonged QT interval and convulsions. Torsade de pointes has been reported in association with combined overdose of oral RISPERDAL and paroxetine.

10.2 Management of Overdosage

In case of acute overdosage, establish and maintain an airway and ensure adequate oxygenation and ventilation. Cardiovascular monitoring should commence immediately and should include continuous electrocardiographic monitoring to detect possible arrhythmias. If antiarrhythmic therapy is administered, disopyramide, procainamide, and quinidine carry a theoretical hazard of QT prolonging effects that might be additive to those of risperidone. Similarly, it is reasonable to expect that the alpha-blocking properties of bretylium might be additive to those of risperidone, resulting in problematic hypotension.

There is no specific antidote to risperidone. Therefore, appropriate supportive measures should be instituted. The possibility of multiple drug involvement should be considered. Hypotension and circulatory collapse should be treated with appropriate measures, such as intravenous fluids and/or sympathomimetic agents (epinephrine and dopamine should not be used, since beta stimulation may worsen hypotension in the setting of risperidone-induced alpha blockade). In cases of severe extrapyramidal symptoms, anticholinergic medication should be administered. Close medical supervision and monitoring should continue until the patient recovers.

11 DESCRIPTION

RISPERDAL CONSTA®contains risperidone, an atypical antipsychotic belonging to the chemical class of benzisoxazole derivatives. The chemical designation is 3-[2-[4-(6-fluoro-1,2-benzisoxazol-3-yl)-1-piperidinyl]ethyl]-6,7,8,9-tetrahydro-2-methyl-4H-pyrido[1,2-a]pyrimidin-4-one. Its molecular formula is C23 H27 FN4O2 and its molecular weight is 410.49. The structural formula is:

Risperidone is practically insoluble in water, freely soluble in methylene chloride, and soluble in methanol and 0.1 NHCl.

RISPERDAL CONSTA (risperidone) Long-Acting Injection is a combination of extended-release microspheres for injection and diluent for parenteral use.

The extended-release microspheres formulation is a white to off-white, free-flowing powder that is available in dosage strengths of 12.5 mg, 25 mg, 37.5 mg, or 50 mg risperidone per vial. Risperidone is micro-encapsulated in 7525 polylactide-co-glycolide (PLG) at a concentration of 381 mg risperidone per gram of microspheres.

The diluent for parenteral use is a clear, colorless solution. Composition of the diluent includes 1 mg/mL citric acid anhydrous, 1.27 mg/mL disodium hydrogen phosphate dihydrate, 1 mg/mL polysorbate 20, 22.5 mg/mL sodium carboxymethyl cellulose, 6 mg/mL sodium chloride, 0.54 mg/mL sodium hydroxide, and water for injection. The microspheres are suspended in the diluent prior to injection.

RISPERDAL CONSTA is provided as a single-use dose pack, consisting of a vial containing the microspheres, a pre-filled syringe containing the diluent, a vial adapter, and two Terumo SurGuard 3 Needles (a 21 G UTW 1-inch needle with needle protection device for deltoid administration and a 20 G TW 2-inch needle with needle protection device for gluteal administration).

12 CLINICAL PHARMACOLOGY

12.1 Mechanism of Action

The mechanism of action of risperidone in schizophrenia is unclear. The drug's therapeutic activity in schizophrenia could be mediated through a combination of dopamine Type 2 (D2) and serotonin Type 2 (5HT2) receptor antagonism. The clinical effect from risperidone results from the combined concentrations of risperidone and its major active metabolite, 9-hydroxyrisperidone (paliperidone) [see Clinical Pharmacology (12.3)] . Antagonism at receptors other than D2 and 5HT2 may explain some of the other effects of risperidone [see Clinical Pharmacology (12.1)] .

12.2 Pharmacodynamics

Risperidone is a monoaminergic antagonist with high affinity (Ki of 0.12 to 7.3 nM) for the serotonin Type 2 (5HT2), dopamine Type 2 (D2), α1 and α2 adrenergic, and H1 histaminergic receptors. Risperidone showed low to moderate affinity (Ki of 47 to 253 nM) for the serotonin 5HT1C, 5HT1D, and 5HT1A receptors, weak affinity (Ki of 620 to 800 nM) for the dopamine D1 and haloperidol-sensitive sigma site, and no affinity (when tested at concentrations >10^-5 M) for cholinergic muscarinic or β1 and β2 adrenergic receptors.

12.3 Pharmacokinetics

Absorption

After a single intramuscular (gluteal) injection of RISPERDAL CONSTA, there is a small initial release of the drug (< 1% of the dose), followed by a lag time of 3 weeks. The main release of the drug starts from 3 weeks onward, is maintained from 4 to 6 weeks, and subsides by 7 weeks following the intramuscular (IM) injection. Therefore, oral antipsychotic supplementation should be given during the first 3 weeks of treatment with RISPERDAL CONSTA to maintain therapeutic levels until the main release of risperidone from the injection site has begun [see Dosage and Administration (2)] . Following single doses of RISPERDAL CONSTA, the pharmacokinetics of risperidone, 9-hydroxyrisperidone (the major metabolite), and risperidone plus 9-hydroxyrisperidone were linear in the dosing range of 12.5 mg to 50 mg.

The combination of the release profile and the dosage regimen (IM injections every 2 weeks) of RISPERDAL CONSTA results in sustained therapeutic concentrations. Steady-state plasma concentrations are reached after 4 injections and are maintained for 4 to 6 weeks after the last injection. Following multiple doses of 25 mg and 50 mg RISPERDAL CONSTA, plasma concentrations of risperidone, 9-hydroxyrisperidone, and risperidone plus 9-hydroxyrisperidone were linear.

Deltoid and gluteal intramuscular injections at the same doses are bioequivalent and, therefore, interchangeable.

Distribution

Once absorbed, risperidone is rapidly distributed. The volume of distribution is 1–2 L/kg. In plasma, risperidone is bound to albumin and α1-acid glycoprotein. The plasma protein binding of risperidone is approximately 90%, and that of its major metabolite, 9-hydroxyrisperidone, is 77%. Neither risperidone nor 9-hydroxyrisperidone displaces each other from plasma binding sites. High therapeutic concentrations of sulfamethazine (100 mcg/mL), warfarin (10 mcg/mL), and carbamazepine (10 mcg/mL) caused only a slight increase in the free fraction of risperidone at 10 ng/mL and of 9-hydroxyrisperidone at 50 ng/mL, changes of unknown clinical significance.

Metabolism and Drug Interactions

Risperidone is extensively metabolized in the liver. The main metabolic pathway is through hydroxylation of risperidone to 9-hydroxyrisperidone by the enzyme, CYP 2D6. A minor metabolic pathway is through N-dealkylation. The main metabolite, 9-hydroxyrisperidone, has similar pharmacological activity as risperidone. Consequently, the clinical effect of the drug results from the combined concentrations of risperidone plus 9-hydroxyrisperidone.

CYP 2D6, also called debrisoquin hydroxylase, is the enzyme responsible for metabolism of many neuroleptics, antidepressants, antiarrhythmics, and other drugs. CYP 2D6 is subject to genetic polymorphism (about 6%–8% of Caucasians, and a very low percentage of Asians, have little or no activity and are "poor metabolizers") and to inhibition by a variety of substrates and some non-substrates, notably quinidine. Extensive CYP 2D6 metabolizers convert risperidone rapidly into 9-hydroxyrisperidone, whereas poor CYP 2D6 metabolizers convert it much more slowly. Although extensive metabolizers have lower risperidone and higher 9-hydroxyrisperidone concentrations than poor metabolizers, the pharmacokinetics of risperidone and 9-hydroxyrisperidone combined, after single and multiple doses, are similar in extensive and poor metabolizers.

The interactions of RISPERDAL CONSTA with coadministration of other drugs have not been systematically evaluated in human subjects. Drug interactions are based primarily on experience with oral RISPERDAL. Risperidone could be subject to two kinds of drug-drug interactions. First, inhibitors of CYP 2D6 interfere with conversion of risperidone to 9-hydroxyrisperidone [see Drug Interactions (7.11)] . This occurs with quinidine, giving essentially all recipients a risperidone pharmacokinetic profile typical of poor metabolizers. The therapeutic benefits and adverse effects of RISPERDAL in patients receiving quinidine have not been evaluated, but observations in a modest number (n≅70) of poor metabolizers given oral RISPERDAL do not suggest important differences between poor and extensive metabolizers. Second, co-administration of carbamazepine and other known enzyme inducers (e.g., phenytoin, rifampin, and phenobarbital) with oral RISPERDAL cause a decrease in the combined plasma concentrations of risperidone and 9-hydroxyrisperidone [see Drug Interactions (7.12)] . It would also be possible for risperidone to interfere with metabolism of other drugs metabolized by CYP 2D6. Relatively weak binding of risperidone to the enzyme suggests this is unlikely [see Drug Interactions (7.11)] .

Excretion

Risperidone and its metabolites are eliminated via the urine and, to a much lesser extent, via the feces. As illustrated by a mass balance study of a single 1 mg oral dose of^14C-risperidone administered as solution to three healthy male volunteers, total recovery of radioactivity at 1 week was 84%, including 70% in the urine and 14% in the feces.

The apparent half-life of risperidone plus 9-hydroxyrisperidone following RISPERDAL CONSTA administration is 3 to 6 days, and is associated with a monoexponential decline in plasma concentrations. This half-life of 3–6 days is related to the erosion of the microspheres and subsequent absorption of risperidone. The clearance of risperidone and risperidone plus 9-hydroxyrisperidone was 13.7 L/h and 5.0 L/h in extensive CYP 2D6 metabolizers, and 3.3 L/h and 3.2 L/h in poor CYP 2D6 metabolizers, respectively. No accumulation of risperidone was observed during long-term use (up to 12 months) in patients treated every 2 weeks with 25 mg or 50 mg RISPERDAL CONSTA. The elimination phase is complete approximately 7 to 8 weeks after the last injection.

Renal Impairment

In patients with moderate to severe renal disease treated with oral RISPERDAL, clearance of the sum of risperidone and its active metabolite decreased by 60% compared with young healthy subjects. Although patients with renal impairment were not studied with RISPERDAL CONSTA, it is recommended that patients with renal impairment be carefully titrated on oral RISPERDAL before treatment with RISPERDAL CONSTA is initiated at a dose of 25 mg. A lower initial dose of 12.5 mg may be appropriate when clinical factors warrant dose adjustment, such as in patients with renal impairment [see Dosage and Administration (2.4)] .

Hepatic Impairment

While the pharmacokinetics of oral RISPERDAL in subjects with liver disease were comparable to those in young healthy subjects, the mean free fraction of risperidone in plasma was increased by about 35% because of the diminished concentration of both albumin and α1-acid glycoprotein. Although patients with hepatic impairment were not studied with RISPERDAL CONSTA, it is recommended that patients with hepatic impairment be carefully titrated on oral RISPERDAL before treatment with RISPERDAL CONSTA is initiated at a dose of 25 mg. A lower initial dose of 12.5 mg may be appropriate when clinical factors warrant dose adjustment, such as in patients with hepatic impairment [see Dosage and Administration (2.4)] .

Elderly

In an open-label trial, steady-state concentrations of risperidone plus 9-hydroxyrisperidone in otherwise healthy elderly patients (≥ 65 years old) treated with RISPERDAL CONSTA for up to 12 months fell within the range of values observed in otherwise healthy nonelderly patients. Dosing recommendations are the same for otherwise healthy elderly patients and nonelderly patients [see Dosage and Administration (2)] .

Race and Gender Effects

No specific pharmacokinetic study was conducted to investigate race and gender effects, but a population pharmacokinetic analysis did not identify important differences in the disposition of risperidone due to gender (whether or not corrected for body weight) or race.

13 NONCLINICAL TOXICOLOGY

13.1 Carcinogenesis, Mutagenesis, Impairment of Fertility

Carcinogenesis - Oral

Risperidone was administered in the diet at doses of 0.63, 2.5, and 10 mg/kg for 18 months to mice and for 25 months to rats. These doses are equivalent to approximately 0.2, 0.75, and 3 times (mice) and 0.4, 1.5, and 6 times (rats) the MRHD of 16 mg/day, based on mg/m^2 body surface area. A maximum tolerated dose was not achieved in male mice. There was a significant increase in pituitary gland adenomas, endocrine pancreatic adenomas, and mammary gland adenocarcinomas. The table below summarizes the multiples of the human dose on mg/m^2 (mg/kg) basis at which these tumors occurred.

 |  |  | Multiples of Maximum Human Dose in mg/m^2 (mg/kg)
Tumor Type | Species | Sex | Lowest Effect Level | Highest No-Effect Level
Pituitary adenomas | mouse | Female | 0.75 (9.4) | 0.2 (2.4)
Endocrine pancreas adenomas | rat | Male | 1.5 (9.4) | 0.4 (2.4)
Mammary gland adenocarcinomas | mouse | Female | 0.2 (2.4) | none
 | rat | Female | 0.4 (2.4) | none
 | rat | Male | 6.0 (37.5) | 1.5 (9.4)
Mammary gland neoplasm, Total | rat | Male | 1.5 (9.4) | 0.4 (2.4)

Antipsychotic drugs have been shown to chronically elevate prolactin levels in rodents. Serum prolactin levels were not measured during the risperidone carcinogenicity studies; however, measurements during subchronic toxicity studies showed that risperidone elevated serum prolactin levels 5–6 fold in mice and rats at the same doses used in the carcinogenicity studies. An increase in mammary, pituitary, and endocrine pancreas neoplasms has been found in rodents after chronic administration of other antipsychotic drugs and is considered to be prolactin-mediated. The relevance for human risk of the findings of prolactin-mediated endocrine tumors in rodents is unclear [see Warnings and Precautions (5.6)] .

Carcinogenesis - Intramuscular

Risperidone was evaluated in a 24-month carcinogenicity study in which SPF Wistar rats were treated every 2 weeks with intramuscular (IM) injections of either 5 mg/kg or 40 mg/kg of risperidone. These doses are 1 and 8 times the MRHD (50 mg) on a mg/m^2 basis. A control group received injections of 0.9% NaCl, and a vehicle control group was injected with placebo microspheres. There was a significant increase in pituitary gland adenomas, endocrine pancreas adenomas, and adrenomedullary pheochromocytomas at 8 times the IM MRHD on a mg/m^2 basis. The incidence of mammary gland adenocarcinomas was significantly increased in female rats at both doses (1 and 8 times the IM MRHD on a mg/m^2 basis). A significant increase in renal tubular tumors (adenoma, adenocarcinomas) was observed in male rats at 8 times the IM MRHD on a mg/m^2 basis. Plasma exposures (AUC) in rats were 0.3 and 2 times (at 5 and 40 mg/kg, respectively) the expected plasma exposure (AUC) at the IM MRHD.

Dopamine D2 receptor antagonists have been shown to chronically elevate prolactin levels in rodents. Serum prolactin levels were not measured during the carcinogenicity studies of oral risperidone; however, measurements taken during subchronic toxicity studies showed that oral risperidone elevated serum prolactin levels 5- to 6-fold in mice and rats at the same doses used in the oral carcinogenicity studies. Serum prolactin levels increased in a dose-dependent manner up to 6- and 1.5-fold in male and female rats, respectively, at the end of the 24-month treatment with risperidone every 2 weeks IM. Increases in the incidence of pituitary gland, endocrine pancreas, and mammary gland neoplasms have been found in rodents after chronic administration of other antipsychotic drugs and may be prolactin-mediated.

The relevance for human risk of the findings of prolactin-mediated endocrine tumors in rodents is unknown [see Warnings and Precautions (5.6)] .

Mutagenesis

No evidence of mutagenic or clastogenic potential for risperidone was found in the in vitrotests of Ames gene mutation, the mouse lymphoma assay, rat hepatocyte DNA-repair assay, the chromosomal aberration test in human lymphocytes, Chinese hamster ovary cells, or in the in vivomicronucleus test in mice, and the sex-linked recessive lethal test in Drosophila.

In addition, no evidence of mutagenic potential was found in the in vitroAmes reverse mutation test for RISPERDAL CONSTA.

Impairment of Fertility

Oral risperidone (0.16 to 5 mg/kg) impaired mating, but not fertility, in rat reproductive studies at doses 0.1 to 3 times the oral maximum recommended human dose (MRHD of 16 mg/day) based on mg/m^2 body surface area. The effect appeared to be in females, since impaired mating behavior was not noted in the male fertility study. In a subchronic study in Beagle dogs in which oral risperidone was administered at doses of 0.31 to 5 mg/kg, sperm motility and concentration were decreased at doses 0.6 to 10 times the oral MRHD on mg/m^2 basis. Dose-related decreases were also noted in serum testosterone at the same doses. Serum testosterone and sperm parameters partially recovered, but remained decreased after treatment was discontinued. A no-effect dose could not be determined in either rat or dog.

14 CLINICAL STUDIES

14.1 Schizophrenia

The effectiveness of RISPERDAL CONSTA in the treatment of schizophrenia was established, in part, on the basis of extrapolation from the established effectiveness of the oral formulation of risperidone. In addition, the effectiveness of RISPERDAL CONSTA in the treatment of schizophrenia was established in a 12-week, placebo-controlled trial in adult psychotic inpatients and outpatients who met the DSM-IV criteria for schizophrenia.

Efficacy data were obtained from 400 patients with schizophrenia who were randomized to receive injections of 25 mg, 50 mg, or 75 mg RISPERDAL CONSTA or placebo every 2 weeks. During a 1-week run-in period, patients were discontinued from other antipsychotics and were titrated to a dose of 4 mg oral RISPERDAL. Patients who received RISPERDAL CONSTA were given doses of oral RISPERDAL (2 mg for patients in the 25-mg group, 4 mg for patients in the 50-mg group, and 6 mg for patients in the 75-mg group) for the 3 weeks after the first injection to provide therapeutic plasma concentrations until the main release phase of risperidone from the injection site had begun. Patients who received placebo injections were given placebo tablets.

Efficacy was evaluated using the Positive and Negative Syndrome Scale (PANSS), a validated, multi-item inventory, composed of five subscales to evaluate positive symptoms, negative symptoms, disorganized thoughts, uncontrolled hostility/excitement, and anxiety/depression.

The primary efficacy variable in this trial was change from baseline to endpoint in the total PANSS score. The mean total PANSS score at baseline for schizophrenic patients in this study was 81.5.

Total PANSS scores showed significant improvement in the change from baseline to endpoint in schizophrenic patients treated with each dose of RISPERDAL CONSTA (25 mg, 50 mg, or 75 mg) compared with patients treated with placebo. While there were no statistically significant differences between the treatment effects for the three dose groups, the effect size for the 75 mg dose group was actually numerically less than that observed for the 50 mg dose group.

Subgroup analyses did not indicate any differences in treatment outcome as a function of age, race, or gender.

14.2 Bipolar Disorder - Monotherapy

The effectiveness of RISPERDAL CONSTA for the maintenance treatment of Bipolar I Disorder was established in a multicenter, double-blind, placebo-controlled study of adult patients who met DSM-IV criteria for Bipolar Disorder Type I, who were stable on medications or experiencing an acute manic or mixed episode.

A total of 501 patients were treated during a 26-week open-label period with RISPERDAL CONSTA (starting dose of 25 mg, and titrated, if deemed clinically desirable, to 37.5 mg or 50 mg; in patients not tolerating the 25 mg dose, the dose could be reduced to 12.5 mg). In the open-label phase, 303 (60%) patients were judged to be stable and were randomized to double-blind treatment with either the same dose of RISPERDAL CONSTA or placebo and monitored for relapse. The primary endpoint was time to relapse to any mood episode (depression, mania, hypomania, or mixed).

Time to relapse was delayed in patients receiving RISPERDAL CONSTA monotherapy as compared to placebo. The majority of relapses were due to manic rather than depressive symptoms. Based on their bipolar disorder history, subjects entering this study had had, on average, more manic episodes than depressive episodes.

14.3 Bipolar Disorder - Adjunctive Therapy

The effectiveness of RISPERDAL CONSTA as an adjunct to treatment with lithium or valproate for the maintenance treatment of Bipolar Disorder was established in a multi-center, randomized, double-blind, placebo-controlled study of adult patients who met DSM-IV criteria for Bipolar Disorder Type I and who experienced at least 4 episodes of mood disorder requiring psychiatric/clinical intervention in the previous 12 months, including at least 2 episodes in the 6 months prior to the start of the study.

A total of 240 patients were treated during a 16-week open-label period with RISPERDAL CONSTA (starting dose of 25 mg, and titrated, if deemed clinically desirable, to 37.5 mg or 50 mg), as adjunctive therapy in addition to continuing their treatment as usual for their bipolar disorder, which consisted of mood stabilizers (primarily lithium and valproate), antidepressants, and/or anxiolytics. All oral antipsychotics were discontinued after the first three weeks of the initial RISPERDAL CONSTA injection. In the open-label phase, 124 (51.7%) were judged to be stable for at least the last 4 weeks and were randomized to double-blind treatment with either the same dose of RISPERDAL CONSTA or placebo in addition to continuing their treatment as usual and monitored for relapse during a 52-week period. The primary endpoint was time to relapse to any new mood episode (depression, mania, hypomania, or mixed).

Time to relapse was delayed in patients receiving adjunctive therapy with RISPERDAL CONSTA as compared to placebo. The relapse types were about half depressive and half manic or mixed episodes.

16 HOW SUPPLIED/STORAGE AND HANDLING

RISPERDAL CONSTA®(risperidone) is available in dosage strengths of 12.5 mg, 25 mg, 37.5 mg, or 50 mg risperidone. It is provided as a single-use dose pack, consisting of a vial containing the risperidone microspheres, a pre-filled syringe containing 2 mL of diluent for RISPERDAL CONSTA, a vial adapter, and two Terumo SurGuard®3 Needles for intramuscular injection (a 21 G UTW 1-inch needle with needle protection device for deltoid administration and a 20 G TW 2-inch needle with needle protection device for gluteal administration).

12.5-mg vial/kit (NDC 50458-309-11): 41 mg (equivalent to 12.5 mg of risperidone) of a white to off-white powder provided in a vial with a violet flip-off cap (NDC 50458-309-01).

25-mg vial/kit (NDC 50458-306-11): 78 mg (equivalent to 25 mg of risperidone) of a white to off-white powder provided in a vial with a pink flip-off cap (NDC 50458-306-01).

37.5-mg vial/kit (NDC 50458-307-11): 116 mg (equivalent to 37.5 mg of risperidone) of a white to off-white powder provided in a vial with a green flip-off cap (NDC 50458-307-01).

50-mg vial/kit (NDC 50458-308-11): 152 mg (equivalent to 50 mg of risperidone) of a white to off-white powder provided in a vial with a blue flip-off cap (NDC 50458-308-01).

Storage and Handling

The entire dose pack should be stored in the refrigerator (36 °F to 46 °F; 2 °C to 8 °C) and protected from light.

If refrigeration is unavailable, RISPERDAL CONSTA can be stored at temperatures not exceeding 77 °F (25 °C) for no more than 7 days prior to administration. Do not expose unrefrigerated product to temperatures above 77 °F (25 °C).

Keep out of reach of children.

17 PATIENT COUNSELING INFORMATION

Physicians are advised to discuss the following issues with patients for whom they prescribe RISPERDAL CONSTA.

Neuroleptic Malignant Syndrome (NMS)

Counsel patients about a potentially fatal adverse reaction, Neuroleptic Malignant Syndrome (NMS), that has been reported in association with administration of antipsychotic drugs. Advise patients, family members, or caregivers to contact the healthcare provider or report to the emergency room if they experience signs and symptoms of NMS, including hyperpyrexia, muscle rigidity, altered mental status including delirium, and evidence of autonomic instability (irregular pulse or blood pressure, tachycardia, diaphoresis, and cardiac dysrhythmia) [see Warnings and Precautions (5.3)] .

Tardive Dyskinesia

Counsel patients on the signs and symptoms of tardive dyskinesia and to contact their healthcare provider if these abnormal movements occur [see Warnings and Precautions (5.4)] .

Metabolic Changes

Educate patients about the risk of metabolic changes, how to recognize symptoms of hyperglycemia and diabetes mellitus and the need for specific monitoring, including blood glucose, lipids, and weight [see Warnings and Precautions (5.5)] .

Orthostatic Hypotension

Educate patients about the risk of orthostatic hypotension and syncope, particularly at the time of initiating treatment, re-initiating treatment, or increasing the dose. [see Warnings and Precautions (5.7)] .

Leukopenia/Neutropenia

Advise patients with a pre-existing low WBC or a history of drug induced leukopenia/neutropenia that they should have their CBC monitored while being treated with RISPERDAL CONSTA [see Warnings and Precautions (5.9)] .

Hyperprolactinemia

Counsel patients on signs and symptoms of hyperprolactinemia that may be associated with chronic use of RISPERDAL CONSTA. Advise them to seek medical attention if they experience any of the following: amenorrhea or galactorrhea in females, erectile dysfunction or gynecomastia in males. [See Warnings and Precautions (5.6)] .

Interference with Cognitive and Motor Performance

Caution patients about performing activities requiring mental alertness, such as operating hazardous machinery, or operating a motor vehicle, until they are reasonably certain that RISPERDAL CONSTA therapy does not affect them adversely [see Warnings and Precautions (5.10)] .

Priapism

Advise patients of the possibility of painful or prolonged penile erections (priapism). Instruct the patient to seek immediate medical attention in the event of priapism [Warnings and Precautions (5.13)].

Heat Exposure and Dehydration

Counsel patients regarding appropriate care in avoiding overheating and dehydration [see Warnings and Precautions (5.14)] .

Concomitant Medication

Advise patients to inform their healthcare providers if they are taking, or plan to take any prescription or over-the-counter drugs, as there is a potential for interactions [see Drug Interactions (7)] .

Alcohol

Advise patients to avoid alcohol during treatment with RISPERDAL CONSTA [see Drug Interactions (7.1)] .

Pregnancy

Advise patients to notify their healthcare provider if they become pregnant or intend to become pregnant during treatment with RISPERDAL CONSTA. Advise patients that RISPERDAL CONSTA may cause extrapyramidal and/or withdrawal symptoms in a neonate. Advise patients that there is a pregnancy registry that monitors pregnancy outcomes in women exposed to RISPERDAL CONSTA during pregnancy [see Use in Specific Populations (8.1)] .

Lactation

Advise breastfeeding women using RISPERDAL CONSTA to monitor infants for somnolence, failure to thrive, jitteriness, and extrapyramidal symptoms (tremors and abnormal muscle movements) and to seek medical care if they notice these signs [see Use in Specific Populations (8.2)] .

Infertility

Advise females of reproductive potential that RISPERDAL CONSTA may impair fertility due to an increase in serum prolactin levels. The effects on fertility are reversible [see Use in Specific Populations (8.3)].

Manufactured for:
Janssen Pharmaceuticals, Inc.
Titusville, NJ 08560, USA

For patent information: www.janssenpatents.com

© Johnson & Johnson and its affiliates 2007

INSTRUCTIONS FOR USE

RISPERDAL CONSTA®
(risperidone)
Long-Acting Injection
12.5 mg, 25 mg, 37.5 mg, 50 mg

For deltoid or gluteal intramuscular injection only
Each injection should be administered by a healthcare professional.

IMPORTANT RESOURCES
For additional information, visit www.risperdalconsta.com or call Janssen Pharmaceuticals, Inc. at 1-800-526-7736.

Manufactured for:
Janssen Pharmaceuticals, Inc.
Titusville, NJ 08560, USA

For patent information: www.janssenpatents.com

© Johnson & Johnson and its affiliates 2007

Revised: 4/2025

Instructions for use

RISPERDAL CONSTA® requires close attention to these step-by-step Instructions for Use to help ensure successful administration.

SINGLE-USE DEVICE

Do not reuse.Medical devices require specific material characteristics to perform as intended. These characteristics have been verified for single use only. Any attempt to re-process the device for subsequent re-use may adversely affect the integrity of the device or lead to deterioration in performance.

Important Information

Use components provided

The components in this dose pack are specifically designed for use with RISPERDAL CONSTA®. RISPERDAL CONSTA® must be reconstituted only in the diluent supplied in the dose pack.

Do not substitute ANY components of the dose pack.

Do not store suspension after reconstitution

Administer dose as soon as possible after reconstitution to avoid settling.

Proper dosing

The entire contents of the vial must be administered to ensure intended dose of RISPERDAL CONSTA®is delivered.

Dose pack contents

Step 1 Assemble components
Take out dose pack | Connect vial adapter to vial
Wait 30 minutes Remove dose pack from the refrigerator and allow to sit at room temperature for at least 30 minutes before reconstituting. Do not warm any other way. | Remove cap from vial Flip off colored cap from vial. Wipe top of the grey stopper with an alcohol swab. Allow to air dry. Do not remove grey rubber stopper. | Prepare vial adapter Hold sterile blister as shown. Peel back and remove paper backing. Do not remove vial adapter from blister. Do not touch spike tip at any time. This will result in contamination. | Connect vial adapter to vial Place vial on a hard surface and hold by the base. Center vial adapter over the grey rubber stopper. Push vial adapter straight down onto vial top until it snaps securely into place. Do not place vial adapter on at an angle or diluent may leak upon transfer to the vial.
Connect prefilled syringe to vial adapter
Remove sterile blister; Keep vial vertical to prevent leakage. Hold base of vial and pull up on the sterile blister to remove. Do not shake. Do not touch exposed luer opening on vial adapter. This will result in contamination. | Use proper grip Hold by white collar at the tip of the syringe. Do not hold syringe by the glass barrel during assembly. | Remove cap Holding the white collar, snap off the white cap. Do not twist or cut off the white cap. Do not touch syringe tip. This will result in contamination.; The broken-off cap can be discarded. | Connect syringe to vial adapter Hold vial adapter by skirt to keep stationary. Hold syringe by white collarthen insert tip into the luer opening of the vial adapter. Do not hold the glass syringe barrel. This may cause the white collar to loosen or detach. Attach the syringe to the vial adapter with a firm clockwise twisting motionuntil it feels snug. Do not over-tighten. Over-tightening may cause the syringe tip to break.

Step 2 Reconstitute microspheres

Inject diluent
Inject entire amount of diluent from syringe into the vial.

Suspend microspheres in diluent
Continuing to hold down the plunger rod, shake vigorously for at least 10 seconds, as shown.
Check the suspension. When properly mixed, the suspension appears uniform, thick and milky in color. Microspheres will be visible in the liquid.
Immediately proceed to the next step so suspension does not settle.

Transfer suspension to syringe
Invert vial completely. Slowly pull plunger rod down to withdraw entire contents from the vial into the syringe.

Remove vial adapter
Hold white collar on the syringe and unscrew from vial adapter.
Tear section of the vial label at the perforation. Apply detached label to the syringe for identification purposes.
Discard both vial and vial adapter appropriately.

Step 3 Attach needle

Select appropriate needle
Choose needle based on injection location (gluteal or deltoid).

Attach needle
Peel blister pouch open part way and use to grasp the base of the needle, as shown.
Holding the white collar on the syringe, attach syringe to needle luer connection with a firm clockwise twisting motionuntil snug.
Do not touch needle luer opening. This will result in contamination.

Resuspend microspheres
Fully remove the blister pouch.
Just before injection, shake syringe vigorously again, as some settling will have occurred.

Step 4 Inject dose

Remove transparent needle protector
Move the needle safety device back towards the syringe, as shown.
Then hold white collar on syringe and carefully pull the transparent needle protector straight off.
Do not twist transparent needle protector, as the luer connection may loosen.

Remove air bubbles
Hold needle upright and tap gently to make any air bubbles rise to the top.
Slowly and carefully press plunger rod upward to remove air.

Inject
Immediately inject entire contents of syringe intramuscularly (IM) into the gluteal or deltoid muscle of the patient.
Gluteal injection should be made into the upper-outer quadrant of the gluteal area.
Do not administer intravenously.

Secure needle in safety device
Using one hand, place needle safety device at a 45-degree angle on a hard, flat surface. Press down with a firm, quick motion until needle is fully engaged in safety device.
Avoid needle stick injury:
Do not use two hands.
Do not intentionally disengage or mishandle the needle safety device.
Do not attempt to straighten the needle or engage the safety device if the needle is bent or damaged.

Properly dispose of needles
Check to confirm needle safety device is fully engaged.
Discard in an approved sharps container.
Also discard the unused needle provided in the dose pack.

PRINCIPAL DISPLAY PANEL - 12.5 mg Kit Carton

12.5 mg
Dose Pack

Store Package
in Refrigerator
(see bottom panel for
storage conditions)

Rx only
Single use only

NDC50458-309-11

Risperdal CONSTA®
risperiDONE Long-Acting Injection

DOSE PACK CONTENTS:

- One 12.5 mg vial of risperidone extended-release microspheres for injection
- One pre-filled syringe containing 2 mL of diluent
- One Vial Adapter
- One 21-gauge UTW 1" Terumo SurGuard®3 safety needle for deltoid injection
- One 20-gauge TW 2" Terumo SurGuard®3 safety needle for gluteal injection

Do not substitute any components of the dose pack.

For deltoid or gluteal intramuscular injection only
Each injection should be administered by a healthcare professional.

PLEASE READ COMPLETE INSTRUCTIONS PRIOR TO USE.

PRINCIPAL DISPLAY PANEL - 25 mg Kit Carton

25 mg
Dose Pack

Store Package
in Refrigerator
(see bottom panel for
storage conditions)

Rx only
Single use only

NDC50458-306-11

Risperdal CONSTA®
risperiDONE Long-Acting Injection

DOSE PACK CONTENTS:

- One 25 mg vial of risperidone extended-release microspheres for injection
- One pre-filled syringe containing 2 mL of diluent
- One Vial Adapter
- One 21-gauge UTW 1" Terumo SurGuard®3 safety needle for deltoid injection
- One 20-gauge TW 2" Terumo SurGuard®3 safety needle for gluteal injection

Do not substitute any components of the dose pack.

For deltoid or gluteal intramuscular injection only
Each injection should be administered by a healthcare professional.

PLEASE READ COMPLETE INSTRUCTIONS PRIOR TO USE.

PRINCIPAL DISPLAY PANEL - 37.5 mg Kit Carton

37.5 mg
Dose Pack

Store Package
in Refrigerator
(see bottom panel for
storage conditions)

Rx only
Single use only

NDC50458-307-11

Risperdal CONSTA®
risperiDONE Long-Acting Injection

DOSE PACK CONTENTS:

- One 37.5 mg vial of risperidone extended-release microspheres for injection
- One pre-filled syringe containing 2 mL of diluent
- One Vial Adapter
- One 21-gauge UTW 1" Terumo SurGuard®3 safety needle for deltoid injection
- One 20-gauge TW 2" Terumo SurGuard®3 safety needle for gluteal injection

Do not substitute any components of the dose pack.

For deltoid or gluteal intramuscular injection only
Each injection should be administered by a healthcare professional.

PLEASE READ COMPLETE INSTRUCTIONS PRIOR TO USE.

PRINCIPAL DISPLAY PANEL - 50 mg Kit Carton

50 mg
Dose Pack

Store Package
in Refrigerator
(see bottom panel for
storage conditions)

Rx only
Single use only

NDC50458-308-11

Risperdal CONSTA®
risperiDONE Long-Acting Injection

DOSE PACK CONTENTS:

- One 50 mg vial of risperidone extended-release microspheres for injection
- One pre-filled syringe containing 2 mL of diluent
- One Vial Adapter
- One 21-gauge UTW 1" Terumo SurGuard®3 safety needle for deltoid injection
- One 20-gauge TW 2" Terumo SurGuard®3 safety needle for gluteal injection

Do not substitute any components of the dose pack.

For deltoid or gluteal intramuscular injection only
Each injection should be administered by a healthcare professional.

PLEASE READ COMPLETE INSTRUCTIONS PRIOR TO USE.